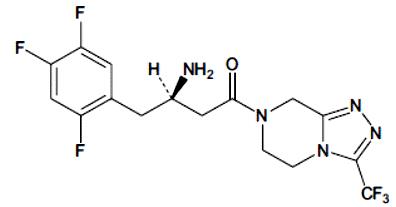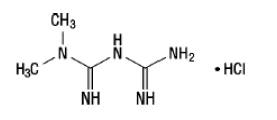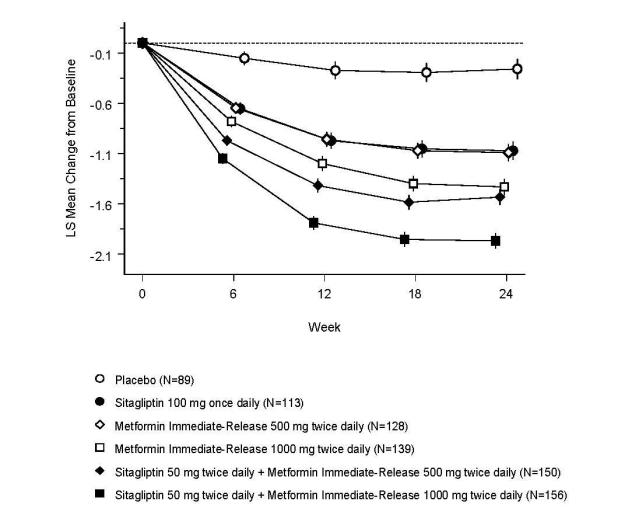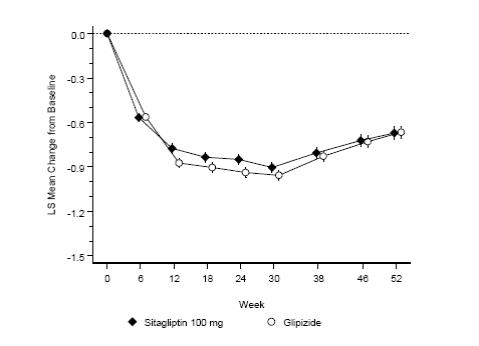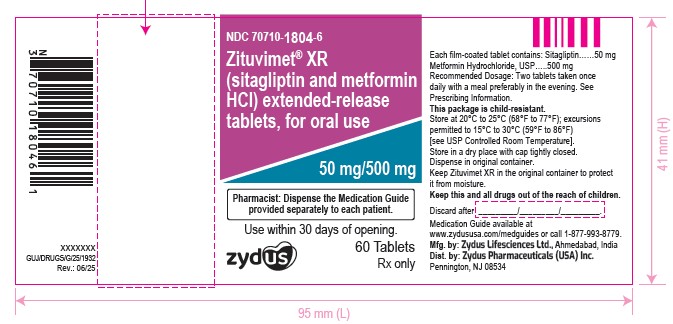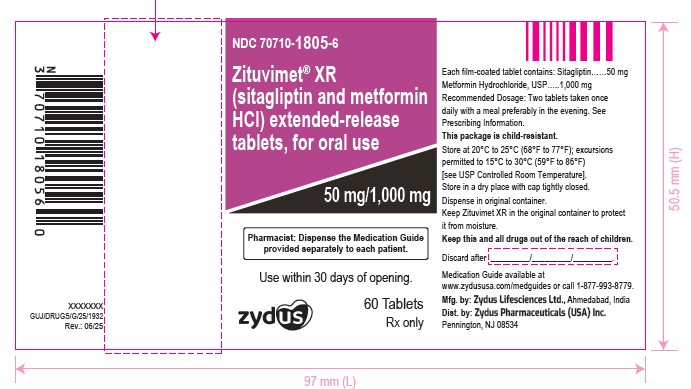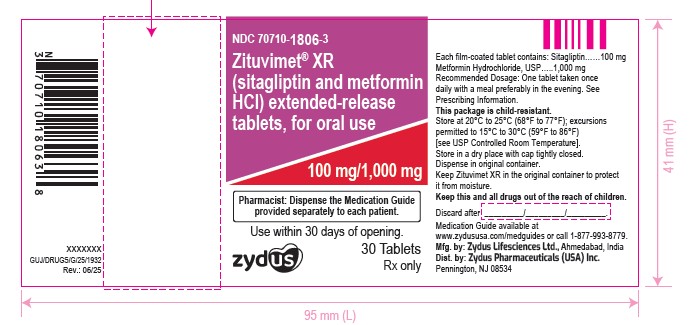 DRUG LABEL: ZITUVIMET XR
NDC: 70710-1805 | Form: TABLET, FILM COATED, EXTENDED RELEASE
Manufacturer: Zydus Pharmaceuticals USA Inc.
Category: prescription | Type: HUMAN PRESCRIPTION DRUG LABEL
Date: 20250716

ACTIVE INGREDIENTS: SITAGLIPTIN 50 mg/1 1; METFORMIN HYDROCHLORIDE 1000 mg/1 1
INACTIVE INGREDIENTS: ANHYDROUS DIBASIC CALCIUM PHOSPHATE; CROSCARMELLOSE SODIUM; FD&C YELLOW NO. 6; FERRIC OXIDE YELLOW; HYPROMELLOSE 2208 (100000 MPA.S); HYPROMELLOSE 2208 (200000 MPA.S); MAGNESIUM STEARATE; MALIC ACID; MICROCRYSTALLINE CELLULOSE; POLYETHYLENE GLYCOL, UNSPECIFIED; POLYVINYL ALCOHOL, UNSPECIFIED; POVIDONE; SILICON DIOXIDE; SODIUM STEARYL FUMARATE; STARCH, CORN; TALC; TITANIUM DIOXIDE

HIGHLIGHTS OF PRESCRIBING INFORMATION

These highlights do not include all the information needed to use ZITUVIMET ®XR safely and effectively. See full prescribing information for ZITUVIMET ®XR.
ZITUVIMET ®XR (sitagliptin and metformin hydrochloride) extended-release tablets, for oral use
Initial U.S. Approval: 2007

BOXED WARNING

WARNING: LACTIC ACIDOSIS

See full prescribing information for complete boxed warning.

- Postmarketing cases of metformin-associated lactic acidosis have resulted in death, hypothermia, hypotension, and resistant bradyarrhythmias. Symptoms included malaise, myalgias, respiratory distress, somnolence, and abdominal pain. Laboratory abnormalities included elevated blood lactate levels, anion gap acidosis, increased lactate/pyruvate ratio, and metformin plasma levels generally >5 mcg/mL. (5.1)
- Risk factors include renal impairment, concomitant use of certain drugs, age ≥65 years old, radiological studies with contrast, surgery and other procedures, hypoxic states, excessive alcohol intake, and hepatic impairment. Steps to reduce the risk of and manage metformin-associated lactic acidosis in these high-risk groups are provided in the Full Prescribing Information. (5.1)
- If lactic acidosis is suspected, discontinue ZITUVIMET XR and institute general supportive measures in a hospital setting. Prompt hemodialysis is recommended. (5.1)

1 INDICATIONS AND USAGE

ZITUVIMET XR is a combination of sitagliptin, a dipeptidyl peptidase-4 (DPP-4) inhibitor, and metformin hydrochloride (HCl), a biguanide indicated as an adjunct to diet and exercise to improve glycemic control in adults with type 2 diabetes mellitus. (1)

Limitations of Use:

- Not for the treatment of type 1 diabetes mellitus. (1)
- Has not been studied in patients with a history of pancreatitis. (1)

2 DOSAGE AND ADMINISTRATION

- Take ZITUVIMET XR orally once daily with a meal. Patients taking two ZITUVIMET XR tablets should take the tablets together. (2.1)
- Individualize the dosage of ZITUVIMET XR on the basis of the patient's current regimen, effectiveness, and tolerability. (2.1)
- The maximum recommended daily dose is 100 mg of sitagliptin and 2,000 mg of metformin HCl extended-release. (2.1)
- The recommended starting dose in patients not currently treated with metformin is 100 mg sitagliptin and 1,000 mg metformin HCl once daily, with gradual dose escalation recommended to reduce gastrointestinal side effects associated with metformin. (2.1)
- The starting dose in patients already treated with metformin should provide sitagliptin dosed as 100 mg and the dose of metformin already being taken once daily. For patients taking metformin HCl 850 mg twice daily or 1,000 mg twice daily, the recommended starting dose of ZITUVIMET XR is two 50 mg sitagliptin and 1,000 mg metformin HCl extended-release tablets once daily. (2.1)
- Maintain the same total daily dose of sitagliptin and metformin when changing between sitagliptin and metformin immediate-release or sitagliptin and metformin extended-release and ZITUVIMET XR. (2.1)
- Prior to initiation, assess renal function with estimated glomerular filtration rate (eGFR) (2.2)
  - Do not use in patients with eGFR below 30 mL/min/1.73 m^2.
  - ZITUVIMET XR is not recommended in patients with eGFR between 30 to 45 mL/min/1.73 m^2.
  - Limit dose of sitagliptin to 50 mg once daily if eGFR falls below 45 mL/min/1.73 m^2.
- ZITUVIMET XR may need to be discontinued at time of, or prior to, iodinated contrast imaging procedures. (2.3)

3 DOSAGE FORMS AND STRENGTHS

ZITUVIMET XR Tablets:

- sitagliptin 100 mg and metformin HCl 1,000 mg extended-release
- sitagliptin 50 mg and metformin HCl 500 mg extended-release
- sitagliptin 50 mg and metformin HCl 1,000 mg extended-release (3)

4 CONTRAINDICATIONS

- Severe renal impairment: eGFR below 30 mL/min/1.73 m^2. (4)
- Metabolic acidosis, including diabetic ketoacidosis. (4)
- History of a serious hypersensitivity reaction to ZITUVIMET XR, sitagliptin, or metformin, such as. anaphylaxis or angioedema) (4)

5 WARNINGS AND PRECAUTIONS

- Lactic Acidosis:See boxed warning. (5.1)
- Pancreatitis:There have been postmarketing reports of acute pancreatitis, including fatal and non-fatal hemorrhagic or necrotizing pancreatitis. If pancreatitis is suspected, promptly discontinue ZITUVIMET XR. (5.2)
- Heart Failure:Has been observed with two other members of the DPP-4 inhibitor class. Consider risks and benefits of ZITUVIMET XR in patients who have known risk factors for heart failure. Monitor patients for signs and symptoms. (5.3)
- Acute Renal Failure:Has been reported postmarketing sometimes requiring dialysis. Before initiating ZITUVIMET XR and at least annually thereafter, assess renal function. (5.4)
- Vitamin B12Deficiency:Metformin may lower vitamin B12levels. Measure hematologic parameters annually and vitamin B12at 2 to 3 year intervals and manage any abnormalities. (5.5)
- Hypoglycemia with Concomitant Use with Insulin or Insulin Secretagogues: Increased risk of hypoglycemia when used in combination with insulin and/or an insulin secretagogue. A lower dose of insulin or insulin secretagogue may be required. (5.6)
- Hypersensitivity Reactions:There have been postmarketing reports of serious allergic and hypersensitivity reactions in patients treated with sitagliptin, such as anaphylaxis, angioedema, and exfoliative skin conditions including Stevens-Johnson syndrome. Promptly stop ZITUVIMET XR, assess for other potential causes, institute appropriate monitoring and treatment. (5.7)
- Severe and Disabling Arthralgia:Has been reported in patients taking DPP-4 inhibitors. Consider as a possible cause for severe joint pain and discontinue drug if appropriate. (5.8)
- Bullous Pemphigoid:There have been postmarketing reports requiring hospitalization in patients taking DPP-4 inhibitors. Tell patients to report development of blisters or erosions. If bullous pemphigoid is suspected, discontinue ZITUVIMET XR. (5.9)

6 ADVERSE REACTIONS

- Most common adverse reactions (incidence ≥5%) of patients simultaneously started on sitagliptin and metformin and more commonly than in patients treated with placebo were diarrhea, upper respiratory tract infection, and headache. (6.1)

To report SUSPECTED ADVERSE REACTIONS, contact Zydus Pharmaceuticals (USA) Inc. at 1-877-993-8779 or FDA at 1-800-FDA-1088 or www.fda.gov/medwatch.

7 DRUG INTERACTIONS

- Carbonic anhydrase inhibitors may increase risk of lactic acidosis. Consider more frequent monitoring. (7)
- Drugs that reduce metformin clearance (such as ranolazine, vandetanib, dolutegravir, and cimetidine) may increase the accumulation of metformin. Consider the benefits and risks of concomitant use. (7)
- Alcohol can potentiate the effect of metformin on lactate metabolism. Warn patients against excessive alcohol intake. (7)

8 USE IN SPECIFIC POPULATIONS

- Females and Males of Reproductive Potential: Advise premenopausal females of the potential for an unintended pregnancy. (8.3)
- Geriatric Use: Assess renal function more frequently. (8.5)
- Hepatic Impairment: Avoid use in patients with hepatic impairment. (8.7)

FULL PRESCRIBING INFORMATION

BOXED WARNING

WARNING: LACTIC ACIDOSIS

Postmarketing cases of metformin-associated lactic acidosis have resulted in death, hypothermia, hypotension, and resistant bradyarrhythmias. The onset of metformin-associated lactic acidosis is often subtle, accompanied only by nonspecific symptoms such as malaise, myalgias, respiratory distress, somnolence, and abdominal pain. Metformin-associated lactic acidosis was characterized by elevated blood lactate levels (>5 mmol/Liter), anion gap acidosis (without evidence of ketonuria or ketonemia), an increased lactate/pyruvate ratio, and metformin plasma levels generally >5 mcg/mL [see Warnings and Precautions (5.1)].

Risk factors for metformin-associated lactic acidosis include renal impairment, concomitant use of certain drugs (e.g., carbonic anhydrase inhibitors such as topiramate), age 65 years old or greater, having a radiological study with contrast, surgery and other procedures, hypoxic states (e.g., acute congestive heart failure), excessive alcohol intake, and hepatic impairment.

Steps to reduce the risk of and manage metformin-associated lactic acidosis in these high risk groups are provided in the full prescribing information [see Dosage and Administration (2.2), Contraindications (4), Warnings and Precautions (5.1), Drug Interactions (7), and Use in Specific Populations (8.6, 8.7)].

If metformin-associated lactic acidosis is suspected, immediately discontinue ZITUVIMET XR and institute general supportive measures in a hospital setting. Prompt hemodialysis is recommended [see Warnings and Precautions (5.1)].

1 INDICATIONS AND USAGE

ZITUVIMET XR is indicated as an adjunct to diet and exercise to improve glycemic control in adults with type 2 diabetes mellitus.

Limitations of Use

ZITUVIMET XR is not recommended in patients with type 1 diabetes mellitus.

ZITUVIMET XR has not been studied in patients with a history of pancreatitis. It is unknown whether patients with a history of pancreatitis are at increased risk for the development of pancreatitis while using ZITUVIMET XR [see Warnings and Precautions (5.2)].

2 DOSAGE AND ADMINISTRATION

2.1 Recommended Dosage and Administration

- Take ZITUVIMET XR orally once daily with a meal. Patients taking two ZITUVIMET XR tablets should take the two tablets together once daily.
- Individualize the dosage of ZITUVIMET XR on the basis of the patient's current regimen, effectiveness, and tolerability.
- The maximum recommended daily dose is 100 mg of sitagliptin and 2,000 mg of metformin hydrochloride (HCl) extended-release.
- The recommended starting dose in patients not currently treated with metformin is 100 mg sitagliptin and 1,000 mg metformin HCl extended-release once daily, with gradual dose escalation recommended to reduce gastrointestinal side effects associated with metformin.
- The starting dose in patients already treated with metformin should provide 100 mg sitagliptin and the previously prescribed dose of metformin.
- For patients taking metformin HCl immediate-release 850 mg twice daily or 1,000 mg twice daily, the recommended starting dose of ZITUVIMET XR is two 50 mg sitagliptin and 1,000 mg metformin HCl extended-release tablets taken together once daily.
- Maintain the same total daily dose of sitagliptin and metformin when changing between sitagliptin and metformin HCl immediate-release or sitagliptin and metformin extended-release and ZITUVIMET XR.
- Do not split, crush or chew ZITUVIMET XR tablets.

2.2 Recommendations for Use in Renal Impairment

- Assess renal function prior to initiation of ZITUVIMET XR and periodically thereafter.
- ZITUVIMET XR is contraindicated in patients with an estimated glomerular filtration rate (eGFR) below 30 mL/min/1.73 m^2 [see Contraindications (4) and Warnings and Precautions (5.1)].
- Initiation of ZITUVIMET XR in patients with an eGFR between 30 and 45 mL/min/1.73 m^2is not recommended.
- In patients taking ZITUVIMET XR whose eGFR later falls below 45 mL/min/1.73 m^2, assess the benefit risk of continuing therapy and limit dose of the sitagliptin component to 50 mg once daily.

2.3 Discontinuation for Iodinated Contrast Imaging Procedures

Discontinue ZITUVIMET XR at the time of, or prior to, an iodinated contrast imaging procedure in patients with an eGFR between 30 and 60 mL/min/1.73 m^2; in patients with a history of liver disease, alcoholism, or heart failure; or in patients who will be administered intra-arterial iodinated contrast. Re-evaluate eGFR 48 hours after the imaging procedure; restart ZITUVIMET XR if renal function is stable [see Warnings and Precautions (5.1)].

3 DOSAGE FORMS AND STRENGTHS

Tablets:

- sitagliptin 100 mg and metformin HCl 1,000 mg extended-release tablets are reddish brown to brown colored, oval shaped, film-coated tablets debossed with "1806" on one side and plain on the other side.
- sitagliptin 50 mg and metformin HCl 500 mg extended-release tablets are light orange to beige colored, oval shaped, film-coated tablets debossed with "1804" on one side and plain on the other side.
- sitagliptin 50 mg and metformin HCl 1,000 mg extended-release tablets are yellow to beige colored, oval shaped, film-coated tablets debossed with "1805" on one side and plain on the other side.

4 CONTRAINDICATIONS

ZITUVIMET XR is contraindicated in patients with:

- Severe renal impairment (eGFR below 30 mL/min/1.73 m^2) [see Warnings and Precautions (5.1)].
- Acute or chronic metabolic acidosis, including diabetic ketoacidosis.
- A history of a serious hypersensitivity reaction to sitagliptin , metformin, or any of the excipients in ZITUVIMET XR. Serious hypersensitivity reactions including anaphylaxis or angioedema have been reported [see Warnings and Precautions (5.7) and Adverse Reactions (6.2)].

5 WARNINGS AND PRECAUTIONS

5.1 Lactic Acidosis

There have been postmarketing cases of metformin-associated lactic acidosis, including fatal cases. These cases had a subtle onset and were accompanied by nonspecific symptoms such as malaise, myalgias, abdominal pain, respiratory distress, or increased somnolence; however, hypothermia, hypotension and resistant bradyarrhythmias have occurred with severe acidosis. Metformin-associated lactic acidosis was characterized by elevated blood lactate concentrations (>5 mmol/Liter), anion gap acidosis (without evidence of ketonuria or ketonemia), and an increased lactate/pyruvate ratio; metformin plasma levels were generally >5 mcg/mL. Metformin decreases liver uptake of lactate increasing lactate blood levels which may increase the risk of lactic acidosis, especially in patients at risk.

If metformin-associated lactic acidosis is suspected, general supportive measures should be instituted promptly in a hospital setting, along with immediate discontinuation of ZITUVIMET XR. In ZITUVIMET XR-treated patients with a diagnosis or strong suspicion of lactic acidosis, prompt hemodialysis is recommended to correct the acidosis and remove accumulated metformin (metformin HCl is dialyzable, with a clearance of up to 170 mL/min under good hemodynamic conditions). Hemodialysis has often resulted in reversal of symptoms and recovery.

Educate patients and their families about the symptoms of lactic acidosis, and if these symptoms occur instruct them to discontinue ZITUVIMET XR and report these symptoms to their health care provider.

For each of the known and possible risk factors for metformin-associated lactic acidosis, recommendations to reduce the risk of and manage metformin-associated lactic acidosis are provided below:

Renal Impairment

The postmarketing metformin-associated lactic acidosis cases primarily occurred in patients with significant renal impairment. The risk of metformin accumulation and metformin-associated lactic acidosis increases with the severity of renal impairment because metformin is substantially excreted by the kidney. Clinical recommendations based upon the patient's renal function include [see Dosage and Administration (2.2) and Clinical Pharmacology (12.3)]:

- Before initiating ZITUVIMET XR, obtain an estimated glomerular filtration rate (eGFR).
- ZITUVIMET XR is contraindicated in patients with an eGFR below 30 mL/min/1.73 m^2 [see Contraindications (4)].
- Initiation of ZITUVIMET XR is not recommended in patients with an eGFR between 30 and less than 45 mL/min/1.73 m^2
- In patients taking ZITUVIMET XR whose eGFR later falls below 45 mL/min/1.73 m^2, assess the benefit and risk of continuing therapy.
- Obtain an eGFR at least annually in all patients taking ZITUVIMET XR. In patients at increased risk for the development of renal impairment (e.g., the elderly), renal function should be assessed more frequently.

Drug Interactions

The concomitant use of ZITUVIMET XR with specific drugs may increase the risk of metformin-associated lactic acidosis: those that impair renal function, result in significant hemodynamic change, interfere with acid-base balance or increase metformin accumulation [see Drug Interactions (7)]. Therefore, consider more frequent monitoring of patients.

Age 65 or Greater

The risk of metformin-associated lactic acidosis increases with the patient's age because elderly patients have a greater likelihood of having hepatic, renal, or cardiac impairment than younger patients. Assess renal function more frequently in elderly patients [see Use in Specific Populations (8.5)].

Radiological Studies with Contrast

Administration of intravascular iodinated contrast agents in metformin-treated patients has led to an acute decrease in renal function and the occurrence of lactic acidosis. Stop ZITUVIMET XR at the time of, or prior to, an iodinated contrast imaging procedure in patients with an eGFR between 30 and 60 mL/min/1.73 m^2; in patients with a history of hepatic impairment, alcoholism, or heart failure; or in patients who will be administered intra-arterial iodinated contrast. Re-evaluate eGFR 48 hours after the imaging procedure, and restart ZITUVIMET XR if renal function is stable.

Surgery and Other Procedures

Withholding of food and fluids during surgical or other procedures may increase the risk for volume depletion, hypotension and renal impairment. ZITUVIMET XR should be temporarily discontinued while patients have restricted food and fluid intake.

Hypoxic States

Several of the postmarketing cases of metformin-associated lactic acidosis occurred in the setting of acute congestive heart failure (particularly when accompanied by hypoperfusion and hypoxemia). Cardiovascular collapse (shock), acute myocardial infarction, sepsis, and other conditions associated with hypoxemia have been associated with lactic acidosis and may also cause prerenal azotemia. When such events occur, discontinue ZITUVIMET XR.

Excessive Alcohol Intake

Alcohol potentiates the effect of metformin on lactate metabolism and this may increase the risk of metformin-associated lactic acidosis. Warn patients against excessive alcohol intake while receiving ZITUVIMET XR.

Hepatic Impairment

Patients with hepatic impairment have developed with cases of metformin-associated lactic acidosis. This may be due to impaired lactate clearance resulting in higher lactate blood levels. Therefore, avoid use of ZITUVIMET XR in patients with clinical or laboratory evidence of hepatic disease.

5.2 Pancreatitis

There have been postmarketing reports of acute pancreatitis, including fatal and non-fatal hemorrhagic or necrotizing pancreatitis, in patients taking sitagliptin with or without metformin. After initiation of ZITUVIMET XR, patients should be observed carefully for signs and symptoms of pancreatitis. If pancreatitis is suspected, ZITUVIMET XR should promptly be discontinued and appropriate management should be initiated. It is unknown whether patients with a history of pancreatitis are at increased risk for the development of pancreatitis while using ZITUVIMET XR.

5.3 Heart Failure

An association between dipeptidyl peptidase-4 (DPP-4) inhibitor treatment and heart failure has been observed in cardiovascular outcomes trials for two other members of the DPP-4 inhibitor class. These trials evaluated patients with type 2 diabetes mellitus and atherosclerotic cardiovascular disease.

Consider the risks and benefits of ZITUVIMET XR prior to initiating treatment in patients at risk for heart failure, such as those with a prior history of heart failure and a history of renal impairment, and observe these patients for signs and symptoms of heart failure during therapy. Advise patients of the characteristic symptoms of heart failure and to immediately report such symptoms. If heart failure develops, evaluate and manage according to current standards of care and consider discontinuation of ZITUVIMET XR.

5.4 Acute Renal Failure

There have been postmarketing reports of worsening renal function in patients taking sitagliptin with or without metformin, including acute renal failure, sometimes requiring dialysis. Before initiation of therapy with ZITUVIMET XR and at least annually thereafter, renal function should be assessed. In patients in whom development of renal dysfunction is anticipated, particularly in elderly patients, renal function should be assessed more frequently and ZITUVIMET XR discontinued if evidence of renal impairment is present. ZITUVIMET XR is contraindicated in patients with severe renal impairment [see Contraindications (4) and Warnings and Precautions (5.1)].

5.5 Vitamin B12 Deficiency

In controlled clinical trials of metformin of 29-week duration, a decrease to subnormal levels of previously normal serum vitamin B12 levels was observed in approximately 7% of patients. Such decrease, possibly due to interference with B12 absorption from the B12-intrinsic factor complex, may be associated with anemia but appears to be rapidly reversible with discontinuation of metformin or vitamin B12 supplementation. Certain individuals (those with inadequate vitamin B12 or calcium intake or absorption) appear to be predisposed to developing subnormal vitamin B12 levels. Measure hematologic parameters on an annual basis and vitamin B12 measurements at 2- to 3-year intervals in patients on ZITUVIMET XR and manage any abnormalities [see Adverse Reactions (6.1)].

5.6 Hypoglycemia with Concomitant Use with Insulin or Insulin Secretagogues

ZITUVIMET XR may increase the risk of hypoglycemia when combined with insulin and/or an insulin secretagogue (e.g., sulfonylurea) [see Adverse Reactions (6)]. A lower dose of insulin or insulin secretagogue may be required to minimize the risk of hypoglycemia when used in combination with ZITUVIMET XR [see Drug Interactions (7)].

5.7 Hypersensitivity Reactions

There have been postmarketing reports of serious hypersensitivity reactions in patients treated with sitagliptin, one of the components of ZITUVIMET XR. These reactions include anaphylaxis, angioedema, and exfoliative skin conditions including Stevens-Johnson syndrome. Onset of these reactions occurred within the first 3 months after initiation of treatment with sitagliptin, with some reports occurring after the first dose. If a hypersensitivity reaction is suspected, discontinue ZITUVIMET XR, assess for other potential causes for the event, and institute alternative treatment for diabetes [see Adverse Reactions (6.2)].

Angioedema has also been reported with other DPP-4 inhibitors Use caution in a patient with a history of angioedema to another DPP-4 inhibitor because it is unknown whether such patients will be predisposed to angioedema with ZITUVIMET XR.

5.8 Severe and Disabling Arthralgia

There have been postmarketing reports of severe and disabling arthralgia in patients taking DPP-4 inhibitors. The time to onset of symptoms following initiation of drug therapy varied from one day to years. Patients experienced relief of symptoms upon discontinuation of the medication. A subset of patients experienced a recurrence of symptoms when restarting the same drug or a different DPP-4 inhibitor. Consider DPP-4 inhibitors as a possible cause for severe joint pain and discontinue drug if appropriate.

5.9 Bullous Pemphigoid

Postmarketing cases of bullous pemphigoid requiring hospitalization have been reported with DPP-4 inhibitor use. In reported cases, patients typically recovered with topical or systemic immunosuppressive treatment and discontinuation of the DPP-4 inhibitor. Tell patients to report development of blisters or erosions while receiving ZITUVIMET XR. If bullous pemphigoid is suspected, ZITUVIMET XR should be discontinued and referral to a dermatologist should be considered for diagnosis and appropriate treatment.

6 ADVERSE REACTIONS

The following adverse reactions are also discussed elsewhere in the prescribing information:

- Lactic Acidosis [see Warnings and Precautions (5.1)]
- Pancreatitis [see Warnings and Precautions (5.2)]
- Heart Failure [see Warnings and Precautions (5.3)]
- Acute Renal Failure [see Warnings and Precautions (5.4)]
- Vitamin B12Deficiency [see Warnings and Precautions (5.5)]
- Hypoglycemia with Concomitant Use with Insulin or Insulin Secretagogues [see Warnings and Precautions (5.6)]
- Hypersensitivity Reactions [see Warnings and Precautions (5.7)]
- Severe and Disabling Arthralgia [see Warnings and Precautions (5.8)]
- Bullous Pemphigoid [see Warnings and Precautions (5.9)]

6.1 Clinical Trials Experience

Because clinical trials are conducted under widely varying conditions, adverse reaction rates observed in the clinical trials of a drug cannot be directly compared to rates in the clinical trials of another drug and may not reflect the rates observed in practice.

Common Adverse Reactions

Sitagliptin and Metformin Immediate-Release Coadministration in Patients with Type 2 Diabetes Mellitus Inadequately Controlled on Diet and Exercise

Table 1 summarizes the most common (≥5% of patients) adverse reactions reported in a 24-week placebo-controlled factorial trial in which sitagliptin and metformin immediate-release were coadministered to patients with type 2 diabetes mellitus inadequately controlled on diet and exercise.

Table 1: Sitagliptin and Metformin Immediate-Release Coadministered to Patients with Type 2 Diabetes Mellitus Inadequately Controlled on Diet and Exercise: Adverse Reactions Reported in ≥5% of Patients Receiving Combination Therapy (and Greater than in Patients Receiving Placebo) [Intent-to-treat population.]
 | Number of Patients (%)
 | Placebo | Sitagliptin 100 mg once daily | Metformin HCl Immediate-Release 500 mg or 1,000 mg twice daily [Data pooled for the patients given the lower and higher doses of metformin.] | Sitagliptin 50 mg twice daily + Metformin HCl Immediate-Release 500 mg or 1,000 mg twice daily
 | N = 176 | N = 179 | N = 364 | N = 372
Diarrhea | 7 (4) | 5 (2.8) | 28 (7.7) | 28 (7.5)
Upper Respiratory Tract Infection | 9 (5.1) | 8 (4.5) | 19 (5.2) | 23 (6.2)
Headache | 5 (2.8) | 2 (1.1) | 14 (3.8) | 22 (5.9)

Sitagliptin Add-on Therapy in Patients with Type 2 Diabetes Mellitus Inadequately Controlled on Metformin

Immediate-Release Alone

In a 24-week placebo-controlled trial of sitagliptin 100 mg administered once daily added to a twice daily metformin immediate-release regimen, there were no adverse reactions reported in ≥5% of patients and more commonly than in patients given placebo. Discontinuation of therapy due to clinical adverse reactions was similar to the placebo treatment group (sitagliptin and metformin immediate-release, 1.9%; placebo and metformin immediate-release, 2.5%).

Gastrointestinal Adverse Reactions

The incidences of pre-selected gastrointestinal adverse experiences in patients treated with sitagliptin and metformin immediate-release were similar to those reported for patients treated with metformin immediate-release alone. See Table 2.

Table 2: Pre-selected Gastrointestinal Adverse Reactions Reported in Patients with Type 2 Diabetes Mellitus Receiving Sitagliptin and Metformin Immediate-Release
 | Number of Patients (%)
 | Trial of Sitagliptin and Metformin Immediate-Release in Patients Inadequately Controlled on Diet and Exercise |  |  |  | Trial of Sitagliptin Add-on in Patients Inadequately Controlled on Metformin Immediate-Release Alone
 | Placebo | Sitagliptin 100 mg once daily | Metformin HCl Immediate-Release 500 mg or 1,000 mg twice daily [Data pooled for the patients given the lower and higher doses of metformin.] | Sitagliptin 50 mg twice daily + Metformin HCl Immediate-Release 500 mg or 1,000 mg twice daily | Placebo and Metformin HCL Immediate- Release ≥1,500 mg daily | Sitagliptin 100 mg once daily and Metformin HCl Immediate- Release ≥1,500 mg daily
 | N = 176 | N = 179 | N = 364 | N = 372 | N = 237 | N = 464
Diarrhea | 7 (4) | 5 (2.8) | 28 (7.7) | 28 (7.5) | 6 (2.5) | 11 (2.4)
Nausea | 2 (1.1) | 2 (1.1) | 20 (5.5) | 18 (4.8) | 2 (0.8) | 6 (1.3)
Vomiting | 1 (0.6) | 0 (0) | 2 (0.5) | 8 (2.2) | 2 (0.8) | 5 (1.1)
Abdominal Pain [Abdominal discomfort was included in the analysis of abdominal pain in the trial of initial therapy.] | 4 (2.3) | 6 (3.4) | 14 (3.8) | 11 (3) | 9 (3.8) | 10 (2.2)

Sitagliptin in Combination with Metformin Immediate-Release and Glimepiride

In a 24-week placebo-controlled trial of sitagliptin 100 mg as add-on therapy in patients with type 2 diabetes mellitus inadequately controlled on metformin immediate-release and glimepiride (sitagliptin, N=116; placebo, N=113), the adverse reactions reported in ≥5% of patients treated with sitagliptin and more commonly than in patients treated with placebo were: hypoglycemia (Table 3) and headache (6.9%, 2.7%).

Sitagliptin in Combination with Metformin Immediate-Release and Rosiglitazone

In a placebo-controlled trial of sitagliptin 100 mg as add-on therapy in patients with type 2 diabetes mellitus inadequately controlled on metformin immediate-release and rosiglitazone (sitagliptin, N=181; placebo, N=97), the adverse reactions reported through Week 18 in ≥5% of patients treated with sitagliptin and more commonly than in patients treated with placebo were: upper respiratory tract infection (sitagliptin, 5.5%; placebo, 5.2%) and nasopharyngitis (6.1%, 4.1%). Through Week 54, the adverse reactions reported in ≥5% of patients treated with sitagliptin and more commonly than in patients treated with placebo were: upper respiratory tract infection (sitagliptin, 15.5%; placebo, 6.2%), nasopharyngitis (11%, 9.3%), peripheral edema (8.3%, 5.2%), and headache (5.5%, 4.1%).

Sitagliptin in Combination with Metformin Immediate-Release and Insulin

In a 24-week placebo-controlled trial of sitagliptin 100 mg as add-on therapy in patients with type 2 diabetes mellitus inadequately controlled on metformin immediate-release and insulin (sitagliptin, N=229; placebo, N=233), the only adverse reaction reported regardless of investigator assessment of causality in ≥5% of patients treated with sitagliptin and more commonly than in patients treated with placebo was hypoglycemia (Table 3).

Hypoglycemia

In the above trials (N=5), adverse reactions of hypoglycemia were based on all reports of symptomatic hypoglycemia; a concurrent glucose measurement was not required although most (77%) reports of hypoglycemia were accompanied by a blood glucose measurement ≤70 mg/dL. When the combination of sitagliptin and metformin immediate-release was coadministered with a sulfonylurea or with insulin, the percentage of patients reporting at least one adverse reaction of hypoglycemia was higher than that observed with placebo and metformin immediate-release coadministered with a sulfonylurea or with insulin (Table 3).

Table 3: Incidence and Rate of Hypoglycemia [Adverse reactions of hypoglycemia were based on all reports of symptomatic hypoglycemia; a concurrent glucose measurement was not required: Intent-to-treat population.] in Placebo-Controlled Clinical Trials of Sitagliptin in Combination with Metformin Immediate-Release Coadministered with Glimepiride or Insulin
Add-On to Glimepiride + Metformin Immediate-Release (24 weeks) | Sitagliptin 100 mg + Metformin Immediate-Release + Glimepiride | Placebo + Metformin Immediate-Release + Glimepiride
 | N = 116 | N = 113
Overall (%) | 19 (16.4) | 1 (0.9)
Rate (episodes/patient-year) [Based on total number of events (i.e., a single patient may have had multiple events).] | 0.82 | 0.02
Severe (%) [Severe events of hypoglycemia were defined as those events requiring medical assistance or exhibiting depressed level/loss of consciousness or seizure.] | 0 (0) | 0 (0)
Add-On to Insulin + Metformin Immediate-Release (24 weeks) | Sitagliptin 100 mg + Metformin Immediate-Release + Insulin | Placebo + Metformin Immediate-Release + Insulin
 | N = 229 | N = 233
Overall (%) | 35 (15.3) | 19 (8.2)
Rate (episodes/patient-year) | 0.98 | 0.61
Severe (%) | 1 (0.4) | 1 (0.4)

The overall incidence of reported adverse reactions of hypoglycemia in patients with type 2 diabetes mellitus inadequately controlled on diet and exercise was 0.6% in patients given placebo, 0.6% in patients given sitagliptin alone, 0.8% in patients given metformin immediate-release alone, and 1.6% in patients given sitagliptin in combination with metformin immediate-release. In patients with type 2 diabetes mellitus inadequately controlled on metformin immediate-release alone, the overall incidence of adverse reactions of hypoglycemia was 1.3% in patients given add-on sitagliptin and 2.1% in patients given add-on placebo.

In the trial of sitagliptin and add-on combination therapy with metformin immediate-release and rosiglitazone, the overall incidence of hypoglycemia was 2.2% in patients given add-on sitagliptin and 0% in patients given add-on placebo through Week 18. Through Week 54, the overall incidence of hypoglycemia was 3.9% in patients given add-on sitagliptin and 1% in patients given add-on placebo.

In an additional 30-week placebo-controlled trial of patients with type 2 diabetes mellitus inadequately controlled with metformin comparing the maintenance of sitagliptin 100 mg versus withdrawal of sitagliptin when initiating basal insulin therapy, the event rate and incidence of documented symptomatic hypoglycemia (blood glucose measurement ≤70 mg/dL) did not differ between the sitagliptin and placebo groups.

Vital Signs and Electrocardiograms

With the combination of sitagliptin and metformin immediate-release, no clinically meaningful changes in vital signs or in electrocardiogram parameters (ECG) (including the QTc interval) were observed.

Pancreatitis

In a pooled analysis of 19 double-blind clinical trials that included data from 10,246 patients randomized to receive sitagliptin 100 mg/day (N=5,429) or corresponding (active or placebo) control (N=4,817), the incidence of acute pancreatitis was 0.1 per 100 patient-years in each group (4 patients with an event in 4,708 patient-years for sitagliptin and 4 patients with an event in 3,942 patient-years for control).

Sitagliptin

The most common adverse experience in sitagliptin monotherapy reported in ≥5% of patients and more commonly than in patients given placebo was nasopharyngitis.

Metformin Extended-Release

In a 24-week clinical trial in which extended-release metformin or placebo was added to glyburide therapy, the most common (>5% and greater than placebo) adverse reactions in the combined treatment group were hypoglycemia (13.7% vs. 4.9%), diarrhea (12.5% vs. 5.6%), and nausea (6.7% vs. 4.2%).

Laboratory Tests

Sitagliptin

The incidence of laboratory adverse reactions was similar in patients treated with sitagliptin and metformin immediate-release (7.6%) compared to patients treated with placebo and metformin (8.7%). In most but not all trials, a small increase in white blood cell count (approximately 200 cells/microL difference in WBC vs. placebo; mean baseline WBC approximately 6,600 cells/microL) was observed due to a small increase in neutrophils. This change in laboratory parameters is not considered to be clinically relevant.

Metformin

In controlled clinical trials of metformin of 29-week duration, a decrease to subnormal levels of previously normal serum vitamin B12 levels, without clinical manifestations, was observed in approximately 7% of patients.

6.2 Postmarketing Experience

Additional adverse reactions have been identified during postapproval use of sitagliptin with metformin, sitagliptin, or metformin. Because these reactions are reported voluntarily from a population of uncertain size, it is generally not possible to reliably estimate their frequency or establish a causal relationship to drug exposure.

Skin and subcutaneous tissue disorders: hypersensitivity reactions including anaphylaxis, angioedema, rash, urticaria, cutaneous vasculitis, bullous pemphigoid, and exfoliative skin conditions including Stevens-Johnson syndrome

Respiratory, thoracic and mediastinal disorders: upper respiratory tract infection

Hepatobiliary disorders: hepatic enzyme elevations; cholestatic, hepatocellular, and mixed hepatocellular liver injury

Gastrointestinal disorders: acute pancreatitis, including fatal and non-fatal hemorrhagic and necrotizing pancreatitis, constipation, vomiting, mouth ulceration, stomatitis

Renal and urinary disorders: worsening renal function, including acute renal failure (sometimes requiring dialysis) and tubulointerstitial nephritis

Musculoskeletal and connective tissue disorders: severe and disabling arthralgia, myalgia, pain in extremity, back pain, pruritus, rhabdomyolysis

Nervous system disorders: headache.

7 DRUG INTERACTIONS

Table 4 presents clinically significant drug interactions with ZITUVIMET XR:

Table 4: Clinically Significant Drug Interactions with ZITUVIMET XR
Carbonic Anhydrase Inhibitors
Clinical Impact: |  | Carbonic anhydrase inhibitors frequently cause a decrease in serum bicarbonate and induce non-anion gap, hyperchloremic metabolic acidosis. Concomitant use of these drugs with ZITUVIMET XR may increase the risk for lactic acidosis.
Intervention: |  | Consider more frequent monitoring of these patients.
Examples: |  | Topiramate, zonisamide, acetazolamide or dichlorphenamide.
Drugs that Reduce Metformin Clearance
Clinical Impact: |  | Concomitant use of drugs that interfere with common renal tubular transport systems involved in the renal elimination of metformin (e.g., organic cationic transporter-2 [OCT2] / multidrug and toxin extrusion [MATE] inhibitors) could increase systemic exposure to metformin and may increase the risk for lactic acidosis [see Clinical Pharmacology (12.3)] .
Intervention: |  | Consider the benefits and risks of concomitant use with ZITUVIMET XR.
Examples: |  | Ranolazine, vandetanib, dolutegravir, and cimetidine.
Alcohol
Clinical Impact: |  | Alcohol is known to potentiate the effect of metformin on lactate metabolism.
Intervention: |  | Warn patients against alcohol intake while receiving ZITUVIMET XR.
Insulin Secretagogues or Insulin
Clinical Impact: |  | Coadministration of ZITUVIMET XR with an insulin secretagogue (e.g., sulfonylurea) or insulin may increase the risk of hypoglycemia.
Intervention: |  | Patients receiving an insulin secretagogue or insulin may require lower doses of the insulin secretagogue or insulin.
Drugs Affecting Glycemic Control
Clinical Impact: | Certain drugs tend to produce hyperglycemia and may lead to loss of glycemic control.
Intervention: | When such drugs are administered to a patient receiving ZITUVIMET XR, observe the patient closely for loss of blood glucose control. When such drugs are withdrawn from a patient receiving ZITUVIMET XR, observe the patient closely for hypoglycemia.
Examples: | Thiazides and other diuretics, corticosteroids, phenothiazines, thyroid products, estrogens, oral contraceptives, phenytoin, nicotinic acid, sympathomimetics, calcium channel blockers, and isoniazid.

8 USE IN SPECIFIC POPULATIONS

8.1 Pregnancy

Risk Summary

The limited available data with ZITUVIMET XR in pregnant women are not sufficient to inform a drug-associated risk for major birth defects and miscarriage. Published studies with metformin use during pregnancy have not reported a clear association with metformin and major birth defect or miscarriage risk [see Data]. There are risks to the mother and fetus associated with poorly controlled diabetes in pregnancy [see Clinical Considerations]. No adverse developmental effects were observed when sitagliptin was administered to pregnant rats and rabbits during organogenesis at oral doses up to 30-times and 20-times, respectively, the 100 mg clinical dose, based on AUC. No adverse developmental effects were observed when metformin was administered to pregnant Sprague Dawley rats and rabbits during organogenesis at doses up to 2- and 6-times, respectively, a 2,000 mg clinical dose, based on body surface area [see Data].

The estimated background risk of major birth defects is 6 to 10% in women with pre-gestational diabetes with a hemoglobin A1c (A1c) >7% and has been reported to be as high as 20 to 25% in women with a A1C >10%. In the U.S. general population, the estimated background risk of major birth defects and miscarriage in clinically recognized pregnancies is 2 to 4% and 15 to 20%, respectively.

Clinical Considerations

Disease-Associated Maternal and/or Embryo/Fetal Risk

Poorly controlled diabetes in pregnancy increases the maternal risk for diabetic ketoacidosis, preeclampsia, spontaneous abortions, preterm delivery, and delivery complications. Poorly controlled diabetes increases the fetal risk for major birth defects, still birth, and macrosomia related morbidity.

Data

Human Data

Published data from post-marketing studies do not report a clear association with metformin and major birth defects, miscarriage, or adverse maternal or fetal outcomes when metformin is used during pregnancy. However, these studies cannot definitely establish the absence of any risk because of methodological limitations, including small sample size and inconsistent comparator groups.

Animal Data

Sitagliptin and Metformin

No animal reproduction studies were conducted with the coadministration of sitagliptin and metformin.

Sitagliptin

In embryo-fetal development studies, sitagliptin administered to pregnant rats and rabbits during organogenesis (gestation day 6 to 20) did not adversely affect developmental outcomes at oral doses up to 250 mg/kg (30-times the 100 mg clinical dose) and 125 mg/kg (20-times the 100 mg clinical dose), respectively, based on AUC. Higher doses in rats associated with maternal toxicity increased the incidence of rib malformations in offspring at 1,000 mg/kg, or approximately 100-times the clinical dose, based on AUC. Placental transfer of sitagliptin was observed in pregnant rats and rabbits.

Sitagliptin administered to female rats from gestation day 6 to lactation day 21 caused no functional or behavioral toxicity in offspring of rats at doses up to 1,000 mg/kg.

Metformin

Metformin did not cause adverse developmental effects when administered to pregnant Sprague Dawley rats and rabbits up to 600 mg/kg/day during the period of organogenesis. This represents an exposure of about 2- and 6-times a 2,000 mg clinical dose based on body surface area (mg/m^2) for rats and rabbits, respectively.

8.2 Lactation

Risk Summary

There is no information regarding the presence of ZITUVIMET XR in human milk, the effects on the breastfed infant, or the effects on milk production. Limited published studies report that metformin is present in human milk [see Data]. There are no reports of adverse effects on breastfed infants exposed to metformin. There is no information on the effects of metformin on milk production. Sitagliptin is present in rat milk and therefore possibly present in human milk [see Data]. The developmental and health benefits of breastfeeding should be considered along with the mother's clinical need for ZITUVIMET XR and any potential adverse effects on the breastfed infant from ZITUVIMET XR or from the underlying maternal condition.

Data

Sitagliptin

Sitagliptin is secreted in the milk of lactating rats at a milk to plasma ratio of 4:1.

Metformin

Published clinical lactation studies report that metformin is present in human milk, which resulted in infant doses approximately 0.11% to 1% of the maternal weight-adjusted dosage and a milk/plasma ratio ranging between 0.13 and 1. However, the studies were not designed to definitely establish the risk of use of metformin during lactation because of small sample size and limited adverse event data collected in infants.

8.3 Females and Males of Reproductive Potential

Discuss the potential for unintended pregnancy with premenopausal women as therapy with metformin may result in ovulation in some anovulatory women.

8.4 Pediatric Use

The safety and effectiveness of ZITUVIMET XR have not been established in pediatric patients.

Three 20-week double-blind, placebo-controlled studies each with 34-week extensions were conducted to evaluate the efficacy and safety of sitagliptin in 410 pediatric patients aged 10 to 17 years with inadequately controlled type 2 diabetes mellitus, with or without insulin therapy (HbA1c 6.5 to 10% for patients not on insulin, HbA1c 7 to 10% for patients on insulin). At study entry, patients in study 1 were not treated with oral antihyperglycemic agents; patients in studies 2 and 3 were on maximally tolerated metformin therapy. The primary efficacy endpoint was the change from baseline in HbA1c after 20 weeks of therapy. The pre-specified primary efficacy analyses included data from study 1 and pooled data from studies 2 and 3, regardless of glycemic rescue or treatment discontinuation.

In both efficacy analyses, the effect of treatment with sitagliptin was not significantly different from placebo. In study 1, the mean baseline HbA1c was 7.5%, and 12% of patients were on insulin therapy. At week 20, the change from baseline in HbA1c in patients treated with sitagliptin (N=95) was 0.06% compared to 0.23% in patients treated with placebo (N=95), a difference of -0.17% (95% CI: -0.62, 0.28). In studies 2 and 3, the mean baseline HbA1c was 8%, 15% of patients were on insulin and 72% were on metformin HCl doses of greater than 1,500 mg daily. At week 20, the change from baseline in HbA1c in patients treated with sitagliptin (N=107) was -0.23% compared to 0.09% in patients treated with placebo (N=113), a difference of -0.33% (95% CI: -0.70, 0.05).

8.5 Geriatric Use

ZITUVIMET XR

In general, dose selection for an elderly patient should be cautious, usually starting at the low end of the dosing range, reflecting the greater frequency of decreased hepatic, renal, or cardiac function, and concomitant disease or other drug therapy and the higher risk of lactic acidosis. Renal function should be assessed more frequently in elderly patients [see Contraindications (4), Warnings and Precautions (5.1, 5.4) and Clinical Pharmacology (12.3)].

Sitagliptin

Of the total number of subjects (N=3,884) in clinical studies of sitagliptin, 725 patients were 65 years and over, while 61 patients were 75 years and over. No overall differences in safety or effectiveness of sitagliptin have been observed between subjects 65 years and over and younger.

Metformin

Controlled clinical studies of metformin did not include sufficient numbers of elderly patients to determine whether they respond differently from younger patients, although other reported clinical experience has not identified differences in responses between the elderly and young patients.

8.6 Renal Impairment

ZITUVIMET XR

The dose of the sitagliptin component should be limited to 50 mg once daily if eGFR falls below 45 mL/min/1.73 m^2. ZITUVIMET XR is contraindicated in severe renal impairment, patients with an eGFR below 30 mL/min/1.73 m^2 [see Dosage and Administration (2.2), Contraindications (4), Warnings and Precautions (5.1) and Clinical Pharmacology (12.3)].

Sitagliptin

Sitagliptin is excreted by the kidney, and sitagliptin exposure is increased in patients with renal impairment [see Clinical Pharmacology (12.3)].

Metformin

Metformin is substantially excreted by the kidney, and the risk of metformin accumulation and lactic acidosis increases with the degree of renal impairment.

8.7 Hepatic Impairment

Use of metformin in patients with hepatic impairment has been associated with some cases of lactic acidosis. ZITUVIMET XR is not recommended in patients with hepatic impairment [see Warnings and Precautions (5.1)].

10 OVERDOSAGE

In the event of overdose with ZITUVIMET XR, consider contacting the Poison Help Line (1-800-222-1222) or a medical toxicologist for additional overdosage management recommendations. Employ supportive measures dictated by the patient's clinical status. Per clinical judgement, consider removal of unabsorbed material from the gastrointestinal tract, and clinical monitoring (including obtaining an ECG).

Sitagliptin is modestly dialyzable. In clinical studies, approximately 13.5% of the dose was removed over a 3- to 4-hour hemodialysis session. Prolonged hemodialysis may be considered if clinically appropriate. It is not known if sitagliptin is dialyzable by peritoneal dialysis.

Overdose of metformin has occurred, including ingestion of amounts greater than 50 grams. Hypoglycemia was reported in approximately 10% of cases, but no causal association with metformin has been established. Lactic acidosis has been reported in approximately 32% of metformin overdose cases [see Warnings and Precautions (5.1)]. Metformin is dialyzable with a clearance of up to 170 mL/min under good hemodynamic conditions. Therefore, hemodialysis may be useful for removal of accumulated drug from patients in whom metformin overdosage is suspected.

11 DESCRIPTION

ZITUVIMET XR tablets for oral use contain two antihyperglycemic medications: sitagliptin and metformin hydrochloride.

Sitagliptin

Sitagliptin is an orally-active inhibitor of the DPP-4 enzyme. Sitagliptin free base drug substance is used to manufacture ZITUVIMET XR. Sitagliptin free base is described chemically as 7-[(3R)-3-amino-1-oxo-4-(2,4,5-trifluorophenyl)butyl]-5,6,7,8-tetrahydro-3-(trifluoromethyl)-1,2,4-triazolo[4,3-α]pyrazine with an empirical formula of C16H15F6N5O and a molecular weight of 407.31. The structural formula is:

Sitagliptin free base is a white to off-white, non-hygroscopic powder. It is soluble in methanol and slightly soluble in water.

Metformin HCl

Metformin HCl (N,N-dimethylimidodicarbonimidic diamide HCl) is a white crystalline powder with a molecular formula of C4H11N5•HCl and a molecular weight of 165.62. Metformin HCl is freely soluble in water, slightly soluble in ethanol (95%), practically insoluble in acetone and in methylene chloride. The pKa of metformin HCl is 12.4. The pH of a 1% aqueous solution of metformin HCl is 6.68. The structural formula is as shown:

ZITUVIMET XR

ZITUVIMET XR is available as film-coated tablets containing:

- 50 mg sitagliptin and 389.93 mg of metformin equivalent to 500 mg metformin HCl (ZITUVIMET XR 50/500).
- 50 mg sitagliptin and 779.86 mg of metformin equivalent to 1,000 mg metformin HCl (ZITUVIMET XR 50/1,000).
- 100 mg sitagliptin and 779.86 mg of metformin equivalent to 1,000 mg metformin HCl (ZITUVIMET XR 100/1,000).

All doses of ZITUVIMET XR contain the following inactive ingredients: colloidal silicon dioxide, croscarmellose sodium, dibasic calcium phosphate anhydrous, ferric oxide yellow, hypromellose, magnesium stearate, malic acid, microcrystalline cellulose, povidone, pregelatinized starch (maize) and sodium stearyl fumarate. In addition, the film-coating for all doses contains the following inactive ingredients: polyethylene glycol, polyvinyl alcohol-partially hydrolyzed, iron oxide yellow, talc and titanium dioxide. Additionally, ZITUVIMET XR 50 mg/500 mg and 100 mg/1,000 mg tablets film-coating contain the inactive ingredient red iron oxide and 50 mg/1,000 mg and 100 mg/1,000 mg tablets film-coating contain the FD&C yellow#6 Aluminum Lake.

12 CLINICAL PHARMACOLOGY

12.1 Mechanism of Action

ZITUVIMET XR

ZITUVIMET XR tablets combine two antihyperglycemic agents: sitagliptin and metformin extended-release.

Sitagliptin

Sitagliptin is a DPP-4 inhibitor, which is believed to exert its actions in patients with type 2 diabetes mellitus by slowing the inactivation of incretin hormones. Concentrations of the active intact hormones are increased by sitagliptin, thereby increasing and prolonging the action of these hormones. Incretin hormones, including glucagon-like peptide-1 (GLP-1) and glucose-dependent insulinotropic polypeptide (GIP), are released by the intestine throughout the day, and levels are increased in response to a meal. These hormones are rapidly inactivated by the enzyme DPP-4. The incretins are part of an endogenous system involved in the physiologic regulation of glucose homeostasis. When blood glucose concentrations are normal or elevated, GLP-1 and GIP increase insulin synthesis and release from pancreatic beta cells by intracellular signaling pathways involving cyclic AMP. GLP-1 also lowers glucagon secretion from pancreatic alpha cells, leading to reduced hepatic glucose production. By increasing and prolonging active incretin levels, sitagliptin increases insulin release and decreases glucagon levels in the circulation in a glucose-dependent manner. Sitagliptin demonstrates selectivity for DPP-4 and does not inhibit DPP-8 or DPP-9 activity in vitro at concentrations approximating those from therapeutic doses.

Metformin

Metformin is a biguanide that improves glucose tolerance in patients with type 2 diabetes mellitus, lowering both basal and postprandial plasma glucose. Metformin decreases hepatic glucose production, decreases intestinal absorption of glucose, and improves insulin sensitivity by increasing peripheral glucose uptake and utilization. With metformin therapy, insulin secretion remains unchanged while fasting insulin levels and day-long plasma insulin response may decrease.

12.2 Pharmacodynamics

Sitagliptin

In patients with type 2 diabetes mellitus, administration of sitagliptin led to inhibition of DPP-4 enzyme activity for a 24-hour period. After an oral glucose load or a meal, this DPP-4 inhibition resulted in a 2- to 3-fold increase in circulating levels of active GLP-1 and GIP, decreased glucagon concentrations, and increased responsiveness of insulin release to glucose, resulting in higher C-peptide and insulin concentrations. The rise in insulin with the decrease in glucagon was associated with lower fasting glucose concentrations and reduced glucose excursion following an oral glucose load or a meal. In studies with healthy subjects, sitagliptin did not lower blood glucose or cause hypoglycemia.

Sitagliptin and Metformin Coadministration

In a two-day study in healthy subjects, sitagliptin alone increased active GLP-1 concentrations, whereas metformin alone increased active and total GLP-1 concentrations to similar extents. Coadministration of sitagliptin and metformin had an additive effect on active GLP-1 concentrations. Sitagliptin, but not metformin, increased active GIP concentrations. It is unclear what these findings mean for changes in glycemic control in patients with type 2 diabetes mellitus.

Cardiac Electrophysiology

In a randomized, placebo-controlled crossover study, 79 healthy subjects were administered a single oral dose of sitagliptin 100 mg, sitagliptin 800 mg (8 times the recommended dose), and placebo. At the recommended dose of 100 mg, there was no effect on the QTc interval obtained at the peak plasma concentration, or at any other time during the study. Following the 800-mg dose, the maximum increase in the placebo-corrected mean change in QTc from baseline at 3 hours postdose was 8.0 msec. This increase is not considered to be clinically significant. At the 800-mg dose, peak sitagliptin plasma concentrations were approximately 11 times higher than the peak concentrations following a 100-mg dose.

In patients with type 2 diabetes mellitus administered sitagliptin 100 mg (N=81) or sitagliptin 200 mg (N=63) daily, there were no meaningful changes in QTc interval based on ECG data obtained at the time of expected peak plasma concentration.

12.3 Pharmacokinetics

ZITUVIMET XR

After administration of two ZITUVIMET XR 50 mg/1,000 mg tablets once daily with the evening meal for 7 days in healthy adult subjects, steady-state for sitagliptin and metformin is reached by Day 4 and 5, respectively.

Sitagliptin

The pharmacokinetics of sitagliptin have been extensively characterized in healthy subjects and patients with type 2 diabetes mellitus. Following a single oral 100-mg dose to healthy volunteers, mean plasma AUC of sitagliptin was 8.52 µM•hr, Cmax was 950 nM, and apparent terminal half-life (t1/2) was 12.4 hours. Plasma AUC of sitagliptin increased in a dose-proportional manner and increased approximately 14% following 100 mg doses at steady-state compared to the first dose. The intra-subject and inter-subject coefficients of variation for sitagliptin AUC were small (5.8% and 15.1%). The pharmacokinetics of sitagliptin was generally similar in healthy subjects and in patients with type 2 diabetes mellitus.

Absorption

ZITUVIMET XR

After administration of ZITUVIMET XR tablets once daily, the median Tmax value for sitagliptin and metformin at steady state is approximately 3 and 8 hours postdose, respectively. The median Tmax value for sitagliptin and metformin after administration of a single tablet of JANUMET is 3 and 3.5 hours postdose, respectively.

Effect of Food

After administration of ZITUVIMET XR tablets with a high-fat breakfast, the AUC for sitagliptin was not altered. The mean Cmax was decreased by 17%, although the median Tmax was unchanged relative to the fasted state. After administration of ZITUVIMET XR with a high-fat breakfast, the AUC for metformin increased 62%, the Cmax for metformin decreased by 9%, and the median Tmax for metformin occurred 2 hours later relative to the fasted state.

Sitagliptin

After oral administration of a 100 mg dose to healthy subjects, sitagliptin was rapidly absorbed with peak plasma concentrations (median Tmax) occurring 1 to 4 hours postdose. The absolute bioavailability of sitagliptin is approximately 87%.

Effect of Food

Coadministration of a high-fat meal with sitagliptin had no effect on the pharmacokinetics of sitagliptin.

Metformin

The absolute bioavailability of a metformin HCl 500-mg tablet given under fasting conditions is approximately 50% to 60%. Studies using single oral doses of metformin HCl tablets 500 mg to 1,500 mg, and 850 mg to 2,550 mg (approximately 1.3 times the maximum recommended daily dosage), indicate that there is a lack of dose proportionality with increasing doses, which is due to decreased absorption rather than an alteration in elimination.

Effect of Food

Food decreases the extent of and slightly delays the absorption of metformin, as shown by approximately a 40% lower mean peak plasma concentration (Cmax), a 25% lower area under the plasma concentration versus time curve (AUC), and a 35-minute prolongation of time to peak plasma concentration (Tmax) following administration of a single 850-mg tablet of metformin HCl with food, compared to the same tablet strength administered fasting. The clinical relevance of these decreases is unknown.

Distribution

Sitagliptin

The mean volume of distribution at steady state following a single 100-mg intravenous dose of sitagliptin to healthy subjects is approximately 198 liters. The fraction of sitagliptin reversibly bound to plasma proteins is low (38%).

Metformin

The apparent volume of distribution (V/F) of metformin following single oral doses of immediate-release metformin HCl tablets 850 mg averaged 654 ± 358 L. Metformin is negligibly bound to plasma proteins. Metformin partitions into erythrocytes, most likely as a function of time. At usual clinical doses and dosing schedules of metformin HCl tablets, steady-state plasma concentrations of metformin are reached within 24 to 48 hours and are generally <1 mcg/mL.

Elimination

Sitagliptin

Approximately 79% of sitagliptin is excreted unchanged in the urine with metabolism being a minor pathway of elimination. The apparent terminal t1/2 following a 100 mg oral dose of sitagliptin was approximately 12.4 hours and renal clearance was approximately 350 mL/min.

Metformin

Following oral administration, approximately 90% of the absorbed drug is eliminated via the renal route within the first 24 hours, with a plasma elimination half-life of approximately 6.2 hours. In blood, the elimination half-life is approximately 17.6 hours, suggesting that the erythrocyte mass may be a compartment of distribution.

Metabolism

Sitagliptin

Following a [^14C] sitagliptin oral dose, approximately 16% of the radioactivity was excreted as metabolites of sitagliptin. Six metabolites were detected at trace levels and are not expected to contribute to the plasma DPP-4 inhibitory activity of sitagliptin. In vitro studies indicated that the primary enzyme responsible for the limited metabolism of sitagliptin was CYP3A4, with contribution from CYP2C8.

Metformin

Intravenous single-dose studies in normal subjects demonstrate that metformin is excreted unchanged in the urine and does not undergo hepatic metabolism (no metabolites have been identified in humans) or biliary excretion. Metabolism studies with extended-release metformin tablets have not been conducted.

Excretion

Sitagliptin

Following administration of an oral [^14C] sitagliptin dose to healthy subjects, approximately 100% of the administered radioactivity was eliminated in feces (13%) or urine (87%) within one week of dosing.

Elimination of sitagliptin occurs primarily via renal excretion and involves active tubular secretion. Sitagliptin is a substrate for human organic anion transporter-3 (hOAT-3), which may be involved in the renal elimination of sitagliptin. The clinical relevance of hOAT-3 in sitagliptin transport has not been established. Sitagliptin is also a substrate of p-glycoprotein (P-gp), which may also be involved in mediating the renal elimination of sitagliptin. However, cyclosporine, a P-gp inhibitor, did not reduce the renal clearance of sitagliptin.

Metformin

Elimination of metformin occurs primarily via renal excretion. Renal clearance is approximately 3.5 times greater than creatinine clearance, which indicates that tubular secretion is the major route of metformin elimination.

Specific Populations

Patients with Renal Impairment

ZITUVIMET XR

Studies characterizing the pharmacokinetics of sitagliptin and metformin after administration of ZITUVIMET XR in renally impaired patients have not been performed [see Dosage and Administration (2.2)].

Sitagliptin

An approximately 2-fold increase in the plasma AUC of sitagliptin was observed in patients with moderate renal impairment with eGFR of 30 to less than 45 mL/min/1.73 m^2, and an approximately 4-fold increase was observed in patients with severe renal impairment including patients with end-stage renal disease (ESRD) on hemodialysis, as compared to normal healthy control subjects [see Dosage and Administration (2.2)].

Metformin

In patients with decreased renal function, the plasma and blood half-life of metformin is prolonged and the renal clearance is decreased [see Contraindications (4) and Warnings and Precautions (5.1)].

Patients with Hepatic Impairment

ZITUVIMET XR

Studies characterizing the pharmacokinetics of sitagliptin and metformin after administration of ZITUVIMET XR in patients with hepatic impairment have not been performed.

Sitagliptin

In patients with moderate hepatic impairment (Child-Pugh score 7 to 9), mean AUC and Cmax of sitagliptin increased approximately 21% and 13%, respectively, compared to healthy matched controls following administration of a single 100-mg dose of sitagliptin. These differences are not considered to be clinically meaningful. There is no clinical experience in patients with severe hepatic impairment (Child-Pugh score >9) [see Use in Specific Populations (8.7)].

Metformin

No pharmacokinetic studies of metformin have been conducted in patients with hepatic impairment.

Effects of Age, Body Mass Index (BMI), Gender, and Race

Sitagliptin

Based on a population pharmacokinetic analysis or a composite analysis of available pharmacokinetic data, BMI, gender, and race do not have a clinically meaningful effect on the pharmacokinetics of sitagliptin. When the effects of age on renal function are taken into account, age alone did not have a clinically meaningful impact on the pharmacokinetics of sitagliptin based on a population pharmacokinetic analysis. Elderly subjects (65 to 80 years) had approximately 19% higher plasma concentrations of sitagliptin compared to younger subjects.

Metformin

Limited data from controlled pharmacokinetic studies of metformin in healthy elderly subjects suggest that total plasma clearance of metformin is decreased, the half-life is prolonged, and Cmax is increased, compared to healthy young subjects. From these data, it appears that the change in metformin pharmacokinetics with aging is primarily accounted for by a change in renal function.

Metformin pharmacokinetic parameters did not differ significantly between normal subjects and patients with type 2 diabetes mellitus when analyzed according to gender. Similarly, in controlled clinical studies in patients with type 2 diabetes mellitus, the antihyperglycemic effect of metformin was comparable in males and females.

No studies of metformin pharmacokinetic parameters according to race have been performed. In controlled clinical studies of metformin in patients with type 2 diabetes mellitus, the antihyperglycemic effect was comparable in Whites (n=249), Black or African Americans (n=51), and Hispanic or Latino ethnicity (n=24).

Drug Interaction Studies

ZITUVIMET XR

Coadministration of multiple doses of sitagliptin (50 mg) and metformin HCl (1,000 mg) given twice daily did not meaningfully alter the pharmacokinetics of either sitagliptin or metformin in patients with type 2 diabetes mellitus.

Pharmacokinetic drug interaction studies with ZITUVIMET XR have not been performed; however, such studies have been conducted with the individual components of ZITUVIMET XR (sitagliptin and metformin extended-release).

Sitagliptin

In Vitro Assessment of Drug Interactions

Sitagliptin is not an inhibitor of CYP isozymes CYP3A4, 2C8, 2C9, 2D6, 1A2, 2C19 or 2B6, and is not an inducer of CYP3A4. Sitagliptin is a P-gp substrate, but does not inhibit P-gp mediated transport of digoxin. Based on these results, sitagliptin is considered unlikely to cause interactions with other drugs that utilize these pathways.

Sitagliptin is not extensively bound to plasma proteins. Therefore, the propensity of sitagliptin to be involved in clinically meaningful drug-drug interactions mediated by plasma protein binding displacement is very low.

In Vivo Assessment of Drug Interactions

Effects of Sitagliptin on Other Drugs

In clinical studies, sitagliptin did not meaningfully alter the pharmacokinetics of metformin, glyburide, simvastatin, rosiglitazone, digoxin, warfarin, or an oral contraception (ethinyl estradiol and norethindrone) (Table 5), providing in vivo evidence of a low propensity for causing drug interactions with substrates of CYP3A4, CYP2C8, CYP2C9, P-gp, and organic cationic transporter (OCT).

Table 5: Effect of Sitagliptin on Systemic Exposure of Coadministered Drugs
Coadministered Drug | Dose of Coadministered Drug* | Dose of Sitagliptin* | Geometric Mean Ratio (ratio with/without sitagliptin) No Effect = 1
Coadministered Drug | Dose of Coadministered Drug* | Dose of Sitagliptin* |  | AUC† | Cmax
Digoxin | 0.25 mg‡ once daily for 10 days | 100 mg‡ once daily for 10 days | Digoxin | 1.11§ | 1.18
Glyburide | 1.25 mg | 200 mg‡ once daily for 6 days | Glyburide | 1.09 | 1.01
Simvastatin | 20 mg | 200 mg‡ once daily for 5 days | Simvastatin | 0.85¶ | 0.8
Simvastatin | 20 mg | 200 mg‡ once daily for 5 days | Simvastatin Acid | 1.12¶ | 1.06
Rosiglitazone | 4 mg | 200 mg‡ once daily for 5 days | Rosiglitazone | 0.98 | 0.99
Warfarin | 30 mg single dose on day 5 | 200 mg‡ once daily for 11 days | S(-) Warfarin | 0.95 | 0.89
Warfarin | 30 mg single dose on day 5 | 200 mg‡ once daily for 11 days | R(+) Warfarin | 0.99 | 0.89
Ethinyl estradiol and norethindrone | 21 days once daily of 35 µg ethinyl estradiol with norethindrone 0.5 mg x 7 days, 0.75 mg x 7 days, 1 mg x 7 days | 200 mg‡ once daily for 21 days | Ethinyl estradiol | 0.99 | 0.97
Ethinyl estradiol and norethindrone | 21 days once daily of 35 µg ethinyl estradiol with norethindrone 0.5 mg x 7 days, 0.75 mg x 7 days, 1 mg x 7 days | 200 mg‡ once daily for 21 days | Norethindrone | 1.03 | 0.98
Metformin HCl | 1,000 mg‡ twice daily for 14 days | 50 mg‡ twice daily for 7 days | Metformin | 1.02@ | 0.97
* All doses administered as single dose unless otherwise specified.
† AUC is reported as AUC0-∞ unless otherwise specified.
‡ Multiple dose.
§ AUC0-24hr.
¶ AUC0-last.
@ AUC0-12hr.

Effects of Other Drugs on Sitagliptin

Clinical data described below suggest that sitagliptin is not susceptible to clinically meaningful interactions by coadministered medications (Table 6).

Table 6: Effect of Coadministered Drugs on Systemic Exposure of Sitagliptin
Coadministered Drug | Dose of Coadministered Drug* | Dose of Sitagliptin* | Geometric Mean Ratio (ratio with/without coadministered drug) No Effect = 1
Coadministered Drug | Dose of Coadministered Drug* | Dose of Sitagliptin* |  | AUC† | Cmax
Cyclosporine | 600 mg once daily | 100 mg once daily | Sitagliptin | 1.29 | 1.68
Metformin HCl | 1,000 mg‡ twice daily for 14 days | 50 mg‡ twice daily for 7 days | Sitagliptin | 1.02§ | 1.05
* All doses administered as single dose unless otherwise specified.
† AUC is reported as AUC0-∞ unless otherwise specified.
‡ Multiple dose.
§ AUC0-12hr.

Metformin

Table 7: Effect of Metformin HCl on Systemic Exposure of Coadministered Drugs
Coadministered Drug | Dose of Coadministered Drug* | Dose of Metformin HCl* | Geometric Mean Ratio (ratio with/without metformin) No Effect = 1
Coadministered Drug | Dose of Coadministered Drug* | Dose of Metformin HCl* |  | AUC† | Cmax
Cimetidine | 400 mg | 850 mg | Cimetidine | 0.95‡ | 1.01
Glyburide | 5 mg | 500 mg§ | Glyburide | 0.78¶ | 0.63¶
Furosemide | 40 mg | 850 mg | Furosemide | 0.87¶ | 0.69¶
Nifedipine | 10 mg | 850 mg | Nifedipine | 1.10‡ | 1.08
Propranolol | 40 mg | 850 mg | Propranolol | 1.01‡ | 0.94
Ibuprofen | 400 mg | 850 mg | Ibuprofen | 0.97@ | 1.01@
* All doses administered as single dose unless otherwise specified
† AUC is reported as AUC0-∞ unless otherwise specified
‡ AUC0-24hr
§ GLUMETZA (metformin HCl extended-release tablets) 500 mg
¶ Ratio of arithmetic means, p value of difference <0.05
@ Ratio of arithmetic means

Table 8: Effect of Coadministered Drugs on Systemic Exposure of Metformin HCl
Coadministered Drug | Dose of Coadministered Drug* | Dose of Metformin HCl* | Geometric Mean Ratio (ratio with/without coadministered drug) No Effect = 1
Coadministered Drug | Dose of Coadministered Drug* | Dose of Metformin HCl* |  | AUC† | Cmax
Glyburide | 5 mg | 500 mg‡ | Metformin‡ | 0.98§ | 0.99§
Furosemide | 40 mg | 850 mg | Metformin | 1.09§ | 1.22§
Nifedipine | 10 mg | 850 mg | Metformin | 1.16 | 1.21
Propranolol | 40 mg | 850 mg | Metformin | 0.90 | 0.94
Ibuprofen | 400 mg | 850 mg | Metformin | 1.05§ | 1.07§
Drugs that are eliminated by renal tubular secretion may increase the accumulation of metformin [see Warnings and Precautions (5.1) and Drug Interactions (7)].
Cimetidine | 400 mg | 850 mg | Metformin | 1.40 | 1.61
Carbonic anhydrase inhibitors may cause metabolic acidosis [see Warnings and Precautions (5.1) and Drug Interactions (7)].
Topiramate | 100 mg¶ | 500 mg¶ | Metformin | 1.25¶ | 1.17
* All doses administered as single dose unless otherwise specified
† AUC is reported as AUC0-∞ unless otherwise specified
‡ GLUMETZA (metformin HCl extended-release tablets) 500 mg
§ Ratio of arithmetic means
¶ Steady state 100 mg Topiramate every 12 hr + metformin HCl 500 mg every 12 hr. AUC = AUC0-12hr

13 NONCLINICAL TOXICOLOGY

13.1 Carcinogenesis, Mutagenesis, Impairment of Fertility

ZITUVIMET XR

No animal studies have been conducted with the combined products in ZITUVIMET XR to evaluate carcinogenesis, mutagenesis or impairment of fertility. The following data are based on the findings in studies with sitagliptin and metformin individually.

Sitagliptin

A two-year carcinogenicity study was conducted in male and female rats given oral doses of sitagliptin of 50, 150, and 500 mg/kg/day. There was an increased incidence of combined liver adenoma/carcinoma in males and females and of liver carcinoma in females at 500 mg/kg. This dose results in exposures approximately 60 times the human exposure at the maximum recommended daily adult human dose (MRHD) of 100 mg/day based on AUC comparisons. Liver tumors were not observed at 150 mg/kg, approximately 20 times the human exposure at the MRHD. A two-year carcinogenicity study was conducted in male and female mice given oral doses of sitagliptin of 50, 125, 250, and 500 mg/kg/day. There was no increase in the incidence of tumors in any organ up to 500 mg/kg, approximately 70 times human exposure at the MRHD. Sitagliptin was not mutagenic or clastogenic with or without metabolic activation in the Ames bacterial mutagenicity assay, a Chinese hamster ovary (CHO) chromosome aberration assay, an in vitro cytogenetics assay in CHO, an in vitro rat hepatocyte DNA alkaline elution assay, and an in vivo micronucleus assay.

In rat fertility studies with oral gavage doses of 125, 250, and 1,000 mg/kg, males were treated for 4 weeks prior to mating, during mating, up to scheduled termination (approximately 8 weeks total), and females were treated 2 weeks prior to mating through gestation day 7. No adverse effect on fertility was observed at 125 mg/kg (approximately 12 times human exposure at the MRHD of 100 mg/day based on AUC comparisons). At higher doses, nondose-related increased resorptions in females were observed (approximately 25 and 100 times human exposure at the MRHD based on AUC comparison).

Metformin

Long-term carcinogenicity studies have been performed in Sprague Dawley rats at doses of 150, 300, and 450 mg/kg/day in males and 150, 450, 900, and 1,200 mg/kg/day in females. These doses are approximately 2, 4, and 8 times in males, and 3, 7, 12, and 16 times in females of the maximum recommended human daily dose of 2,000 mg based on body surface area comparisons. No evidence of carcinogenicity with metformin was found in either male or female rats. A carcinogenicity study was also performed in Tg.AC transgenic mice at doses up to 2,000 mg applied dermally. No evidence of

carcinogenicity was observed in male or female mice.

Genotoxicity assessments in the Ames test, gene mutation test (mouse lymphoma cells), chromosomal aberrations test (human lymphocytes) and in vivo mouse micronucleus tests were negative. Fertility of male or female rats was not affected by metformin when administered at doses up to 600 mg/kg/day, which is approximately 3 times the maximum recommended human daily dose based on body surface area comparisons.

14 CLINICAL STUDIES

The coadministration of sitagliptin and metformin immediate-release has been evaluated in patients with type 2 diabetes mellitus inadequately controlled on diet and exercise and in combination with other anti-hyperglycemic medications.

Metformin Extended-Release Compared to Metformin Immediate-Release in Patients with Type 2 Diabetes Mellitus

In a multicenter, randomized, double-blind, active-controlled, dose-ranging, parallel group trial extended-release metformin HCl 1,500 mg once daily, extended-release metformin HCl 1,500 mg per day in divided doses (500 mg in the morning and 1,000 mg in the evening), and extended-release metformin HCl 2,000 mg once daily were compared to immediate-release metformin HCl 1,500 mg per day in divided doses (500 mg in the morning and 1,000 mg in the evening). This trial enrolled patients (n = 338) who were newly diagnosed with diabetes, patients treated only with diet and exercise, patients treated with a single antidiabetic medication (sulfonylureas, alpha-glucosidase inhibitors, thiazolidinediones, or meglitinides), and patients (n = 368) receiving metformin HCl up to 1,500 mg/day plus a sulfonylurea at a dose equal to or less than one-half the maximum dose. Patients who were enrolled on monotherapy or combination antidiabetic therapy underwent a 6-week washout. Patients randomized to extended-release metformin HCl began titration from 1,000 mg/day up to their assigned treatment dose over 3 weeks. Patients randomized to immediate-release metformin HCl initiated 500 mg twice daily for 1 week followed by 500 mg with breakfast and 1,000 mg with dinner for the second week. The 3-week treatment period was followed by an additional 21-week period at the randomized dose. For HbA1c and fasting plasma glucose, each of the extended-release metformin regimens was at least as effective as immediate-release metformin. Additionally, once daily dosing of extended-release metformin was as effective as twice daily dosing of the immediate-release metformin formulation.

Sitagliptin and Metformin Immediate-Release Coadministration in Patients with Type 2 Diabetes Mellitus Inadequately Controlled on Diet and Exercise

A total of 1,091 patients with type 2 diabetes mellitus and inadequate glycemic control on diet and exercise participated in a 24-week, randomized, double-blind, placebo-controlled factorial trial designed to assess the efficacy of sitagliptin and metformin immediate-release coadministration. Patients on an antihyperglycemic agent (N=541) underwent a diet, exercise, and drug washout period of up to 12 weeks duration. After the washout period, patients with inadequate glycemic control (A1C 7.5% to 11%) were randomized after completing a 2-week single-blind placebo run-in period. Patients not on antihyperglycemic agents at trial entry (N=550) with inadequate glycemic control (A1C 7.5% to 11%) immediately entered the 2-week single-blind placebo run-in period and then were randomized. Approximately equal numbers of patients were randomized to receive placebo, 100 mg of sitagliptin once daily, 500 mg or 1,000 mg of metformin HCl immediate-release twice daily, or 50 mg of sitagliptin twice daily in combination with 500 mg or 1,000 mg of metformin HCl immediate-release twice daily. Patients who failed to meet specific glycemic goals during the trial were treated with glyburide (glibenclamide) rescue.

Sitagliptin and metformin immediate-release coadministration provided significant improvements in A1C, FPG, and 2-hour PPG compared to placebo, to metformin immediate-release alone, and to sitagliptin alone (Table 9, Figure 1). For patients not on an anti-hyperglycemic agent at trial entry, mean reductions from baseline in A1C were: sitagliptin 100 mg once daily, -1.1%; metformin HCl immediate-release 500 mg bid, -1.1%; metformin HCl immediate-release 1,000 mg bid, -1.2%; sitagliptin 50 mg bid with metformin HCl immediate-release 500 mg bid, -1.6%; sitagliptin 50 mg bid with metformin HCl immediate-release 1,000 mg bid, -1.9%; and for patients receiving placebo, -0.2%. Lipid effects were generally neutral. The decrease in body weight in the groups given sitagliptin in combination with metformin immediate-release was similar to that in the groups given metformin alone or placebo.

Table 9: Glycemic Parameters at Final Visit (24-Week Trial) for Sitagliptin and Metformin Immediate-Release, Alone and in Combination in Patients with Type 2 Diabetes Mellitus Inadequately Controlled on Diet and Exercise [Intent-to-treat population using last observation in the trial prior to glyburide (glibenclamide) rescue therapy.]
 | Placebo | Sitagliptin 100 mg once daily | Metformin HCl Immediate-Release 500 mg twice daily | Metformin HCl Immediate-Release 1,000 mg twice daily | Sitagliptin 50 mg bid + Metformin HCl Immediate-Release 500 mg twice daily | Sitagliptin 50 mg bid + Metformin HCl Immediate-Release 1,000 mg twice daily
A1C (%) | N = 165 | N = 175 | N = 178 | N = 177 | N = 183 | N = 178
Baseline (mean) | 8.7 | 8.9 | 8.9 | 8.7 | 8.8 | 8.8
Change from baseline (adjusted mean [Least squares means adjusted for prior antihyperglycemic therapy status and baseline value.]) | 0.2 | -0.7 | -0.8 | -1.1 | -1.4 | -1.9
Difference from placebo (adjusted mean) |  | -0.8 [p<0.001 compared to placebo.] | -1 | -1.3 | -1.6 | -2.1
(95% CI) |  | (-1.1, -0.6) | (-1.2, -0.8) | (-1.5, -1.1) | (-1.8, -1.3) | (-2.3, -1.8)
Patients (%) achieving A1C <7% | 15 (9%) | 35 (20%) | 41 (23%) | 68 (38%) | 79 (43%) | 118 (66%)
% Patients receiving rescue medication | 32 | 21 | 17 | 12 | 8 | 2
FPG (mg/dL) | N = 169 | N = 178 | N = 179 | N = 179 | N = 183 | N = 180
Baseline (mean) | 196 | 201 | 205 | 197 | 204 | 197
Change from baseline (adjusted mean) | 6 | -17 | -27 | -29 | -47 | -64
Difference from placebo (adjusted mean) |  | -23 | -33 | -35 | -53 | -70
(95% CI) |  | (-33, -14) | (-43, -24) | (-45, -26) | (-62, -43) | (-79, -60)
2-hour PPG (mg/dL) | N = 129 | N = 136 | N = 141 | N = 138 | N = 147 | N = 152
Baseline (mean) | 277 | 285 | 293 | 283 | 292 | 287
Change from baseline (adjusted mean) | 0 | -52 | -53 | -78 | -93 | -117
Difference from placebo (adjusted mean) |  | -52 | -54 | -78 | -93 | -117
(95% CI) |  | (-67, -37) | (-69, -39) | (-93, -63) | (-107, -78) | (-131, -102)

Figure 1: Mean Change from Baseline for A1C (%) over 24 Weeks with Sitagliptin and Metformin Immediate-Release, Alone and in Combination in Patients with Type 2 Diabetes Mellitus Inadequately Controlled with Diet and Exercise*

* All Patients Treated Population: least squares means adjusted for prior antihyperglycemic therapy and baseline value.

Initial combination therapy or maintenance of combination therapy should be individualized and are left

to the discretion of the health care provider.

Sitagliptin Add-on Therapy in Patients with Type 2 Diabetes Mellitus Inadequately Controlled on Metformin Immediate-Release Alone

A total of 701 patients with type 2 diabetes mellitus participated in a 24-week, randomized, double-blind, placebo-controlled trial designed to assess the efficacy of sitagliptin in combination with metformin immediate-release. Patients already on metformin HCl immediate-release (N=431) at a dose of at least 1,500 mg per day were randomized after completing a 2-week, single-blind placebo run-in period. Patients on metformin immediate-release and another antihyperglycemic agent (N=229) and patients not on any antihyperglycemic agents (off therapy for at least 8 weeks, N=41) were randomized after a run-in period of approximately 10 weeks on metformin HCl immediate-release (at a dose of at least 1,500 mg per day) in monotherapy. Patients were randomized to the addition of either 100 mg of sitagliptin or placebo, administered once daily. Patients who failed to meet specific glycemic goals during the trials were treated with pioglitazone rescue.

In combination with metformin immediate-release, sitagliptin provided significant improvements in A1C, FPG, and 2-hour PPG compared to placebo with metformin immediate-release (Table 10). Rescue glycemic therapy was used in 5% of patients treated with sitagliptin 100 mg and 14% of patients treated with placebo. A similar decrease in body weight was observed for both treatment groups.

Table 10: Glycemic Parameters at Final Visit (24-Week Trial) of Sitagliptin as Add-on Combination Therapy with Metformin Immediate-Release [Intent-to-treat population using last observation in the trial prior to pioglitazone rescue therapy.]
 | Sitagliptin 100 mg once daily + Metformin Immediate-Release | Placebo + Metformin Immediate-Release
A1C (%) | N = 453 | N = 224
Baseline (mean) | 8 | 8
Change from baseline (adjusted mean [Least squares means adjusted for prior antihyperglycemic therapy and baseline value.]) | -0.7 | -0
Difference from placebo + metformin immediate-release (adjusted mean) (95% CI) | -0.7 [p<0.001 compared to placebo + metformin.] (-0.8, -0.5)
Patients (%) achieving A1C <7% | 213 (47%) | 41 (18%)
FPG (mg/dL) | N = 454 | N = 226
Baseline (mean) | 170 | 174
Change from baseline (adjusted mean) | -17 | 9
Difference from placebo + metformin immediate-release | -25
(adjusted mean) (95% CI) | (-31, -20)
2-hour PPG (mg/dL) | N = 387 | N = 182
Baseline (mean) | 275 | 272
Change from baseline (adjusted mean) | -62 | -11
Difference from placebo + metformin immediate-release | -51
(adjusted mean) (95% CI) | (-61, -41)

Sitagliptin Add-on Therapy in Patients with Type 2 Diabetes Mellitus Inadequately Controlled on the

Combination of Metformin Immediate-Release and Glimepiride

A total of 441 patients with type 2 diabetes mellitus participated in a 24-week, randomized, double-blind, placebo-controlled trial designed to assess the efficacy of sitagliptin in combination with glimepiride, with or without metformin immediate-release. Patients entered a run-in treatment period on glimepiride (≥4 mg per day) alone or glimepiride in combination with metformin HCl immediate-release (≥1,500 mg per day). After a dose-titration and dose-stable run-in period of up to 16 weeks and a 2-week placebo run-in period, patients with inadequate glycemic control (A1C 7.5% to 10.5%) were randomized to the addition of either 100 mg of sitagliptin or placebo, administered once daily. Patients who failed to meet specific glycemic goals during the trials were treated with pioglitazone rescue.

Patients receiving sitagliptin with metformin immediate-release and glimepiride had significant improvements in A1C and FPG compared to patients receiving placebo with metformin immediate-release and glimepiride (Table 11), with mean reductions from baseline relative to placebo in A1C of -0.9% and in FPG of -21 mg/dL. Rescue therapy was used in 8% of patients treated with add-on sitagliptin 100 mg and 29% of patients treated with add-on placebo. The patients treated with add-on sitagliptin had a mean increase in body weight of 1.1 kg vs. add-on placebo (+0.4 kg vs. -0.7 kg). In addition, add-on sitagliptin resulted in an increased rate of hypoglycemia compared to add-on placebo [see Warnings and Precautions (5.6) and Adverse Reactions (6.1)].

Table 11: Glycemic Parameters at Final Visit (24-Week Trial) for Sitagliptin in Combination with Metformin Immediate-Release and Glimepiride [Intent-to-treat population using last observation in the trial prior to pioglitazone rescue therapy.]
 | Sitagliptin 100 mg + Metformin Immediate-Release and Glimepiride | Placebo + Metformin Immediate-Release and Glimepiride
A1C (%) | N = 115 | N = 105
Baseline (mean) | 8.3 | 8.3
Change from baseline (adjusted mean [Least squares means adjusted for prior antihyperglycemic therapy status and baseline value.]) | -0.6 | 0.3
Difference from placebo (adjusted mean) (95% CI) | -0.9 [p<0.001 compared to placebo.] (-1.1, -0.7)
Patients (%) achieving A1C <7% | 26 (23%) | 1 (1%)
FPG (mg/dL) | N = 115 | N = 109
Baseline (mean) | 179 | 179
Change from baseline (adjusted mean) | -8 | 13
Difference from placebo (adjusted mean) (95% CI) | -21 (-32, -10)

Sitagliptin Add-on Therapy in Patients with Type 2 Diabetes Mellitus Inadequately Controlled on the

Combination of Metformin Immediate-Release and Rosiglitazone

A total of 278 patients with type 2 diabetes mellitus participated in a 54-week, randomized, double-blind, placebo-controlled trial designed to assess the efficacy of sitagliptin in combination with metformin immediate-release and rosiglitazone. Patients on dual therapy with metformin HCl immediate-release ≥1,500 mg/day and rosiglitazone ≥4 mg/day or with metformin HCl immediate-release ≥1,500 mg/day and pioglitazone ≥30 mg/day (switched to rosiglitazone ≥4 mg/day) entered a dose-stable run-in period of 6 weeks. Patients on other dual therapy were switched to metformin HCl immediate-release ≥1,500 mg/day and rosiglitazone ≥4 mg/day in a dose titration/stabilization run-in period of up to 20 weeks in duration. After the run-in period, patients with inadequate glycemic control (A1C 7.5% to 11%) were randomized 2:1 to the addition of either 100 mg of sitagliptin or placebo, administered once daily. Patients who failed to meet specific glycemic goals during the trials were treated with glipizide (or other sulfonylurea) rescue. The primary time point for evaluation of glycemic parameters was Week 18.

In combination with metformin immediate-release and rosiglitazone, sitagliptin provided significant improvements in A1C, FPG, and 2-hour PPG compared to placebo with metformin immediate-release and rosiglitazone (Table 12) at Week 18. At Week 54, mean reduction in A1C was -1% for patients treated with sitagliptin and -0.3% for patients treated with placebo in an analysis based on the intent-to-treat population. Rescue therapy was used in 18% of patients treated with sitagliptin 100 mg and 40% of patients treated with placebo. There was no significant difference between sitagliptin and placebo in body weight change.

Table 12: Glycemic Parameters at Week 18 for Sitagliptin in Add-on Combination Therapy with Metformin Immediate-Release and Rosiglitazone [Intent-to-treat population using last observation in the trial prior to glipizide (or other sulfonylurea) rescue therapy.]
 | Week 18
 | Sitagliptin 100 mg + Metformin Immediate- Release + Rosiglitazone | Placebo + Metformin Immediate-Release + Rosiglitazone
A1C (%) | N = 176 | N = 93
Baseline (mean) | 8.8 | 8.7
Change from baseline (adjusted mean [Least squares means adjusted for prior antihyperglycemic therapy status and baseline value.]) | -1 | -0.4
Difference from placebo + rosiglitazone + metformin immediate-release (adjusted mean) (95% CI) | -0.7 [p<0.001 compared to placebo + metformin + rosiglitazone.] (-0.9, -0.4)
Patients (%) achieving A1C <7% | 39 (22%) | 9 (10%)
FPG (mg/dL) | N = 179 | N = 94
Baseline (mean) | 181 | 182
Change from baseline (adjusted mean) | -30 | -11
Difference from placebo + rosiglitazone + metformin immediate-release (adjusted mean) (95% CI) | -18 (-26, -10)
2-hour PPG (mg/dL) | N = 152 | N = 80
Baseline (mean) | 256 | 248
Change from baseline (adjusted mean) | -59 | -21
Difference from placebo + rosiglitazone + metformin immediate-release (adjusted mean) (95% CI) | -39 (-51, -26)

Sitagliptin Add-on Therapy in Patients with Type 2 Diabetes Mellitus Inadequately Controlled on the Combination of Metformin Immediate-Release and Insulin

A total of 641 patients with type 2 diabetes mellitus participated in a 24-week, randomized, double-blind, placebo-controlled trial designed to assess the efficacy of sitagliptin as add-on to insulin therapy. Approximately 75% of patients were also taking metformin immediate-release. Patients entered a 2-week, single-blind run-in treatment period on pre-mixed, long-acting, or intermediate-acting insulin, with or without metformin HCl immediate-release (≥1,500 mg per day). Patients using short-acting insulins were excluded unless the short-acting insulin was administered as part of a pre-mixed insulin. After the run-in period, patients with inadequate glycemic control (A1C 7.5% to 11%) were randomized to the addition of either 100 mg of sitagliptin (N=229) or placebo (N=233), administered once daily. Patients were on a stable dose of insulin prior to enrollment with no changes in insulin dose permitted during the run-in period. Patients who failed to meet specific glycemic goals during the double-blind treatment period were to have uptitration of the background insulin dose as rescue therapy.

Among patients also receiving metformin immediate-release, the median daily insulin (pre-mixed, intermediate or long acting) dose at baseline was 40 units in the sitagliptin-treated patients and 42 units in the placebo-treated patients. The median change from baseline in daily dose of insulin was zero for both groups at the end of the trial. Patients receiving sitagliptin with metformin immediate-release and insulin had significant improvements in A1C, FPG and 2-hour PPG compared to patients receiving placebo with metformin immediate-release and insulin (Table 13). The adjusted mean change from baseline in body weight was -0.3 kg in patients receiving sitagliptin with metformin immediate-release and insulin and -0.2 kg in patients receiving placebo with metformin immediate-release and insulin. There was an increased rate of hypoglycemia in patients treated with sitagliptin [see Warnings and Precautions (5.6) and Adverse Reactions (6.1)].

Table 13: Glycemic Parameters at Final Visit (24-Week Trial) for Sitagliptin as Add-on Combination Therapy with Metformin Immediate-Release and Insulin*
 | Sitagliptin 100 mg + Metformin Immediate-Release + Insulin | Placebo + Metformin Immediate-Release + Insulin
A1C (%) | N = 223 | N = 229
Baseline (mean) | 8.7 | 8.6
Change from baseline (adjusted mean†, ‡) | -0.7 | -0.1
Difference from placebo (adjusted mean†) (95% CI) | -0.5@ (-0.7, -0.4)
Patients (%) achieving A1C <7% | 32 (14%) | 12 (5%)
FPG (mg/dL) | N = 225 | N = 229
Baseline (mean) | 173 | 176
Change from baseline (adjusted mean†) | -22 | -4
Difference from placebo (adjusted mean†) (95% CI) | -18@ (-28, -8.4)
2-hour PPG (mg/dL) | N = 182 | N = 189
Baseline (mean) | 281 | 281
Change from baseline (adjusted mean†) | -39 | 1
Difference from placebo (adjusted mean†) (95% CI) | -40@ (-53, -28)
* Intent-to-treat population using last observation in the trial prior to rescue therapy.
† Least squares means adjusted for insulin use at the screening visit, type of insulin used at the screening visit (premixed vs. non pre-mixed [intermediate- or long-acting]), and baseline value.
‡ Treatment by insulin stratum interaction was not significant (p>0.10).
@ p<0.001 compared to placebo.

Maintenance of Sitagliptin During Initiation and Titration of Insulin Glargine

A total of 746 patients with type 2 diabetes mellitus (mean baseline HbA1C 8.8%, disease duration 10.8 years) participated in a 30-week, randomized, double-blind, placebo-controlled trial to assess the efficacy and safety of continuing sitagliptin during the initiation and up-titration of insulin glargine. Patients who were on a stable dose of metformin HCl (≥1,500 mg/day) in combination with a DPP-4 inhibitor and/or sulfonylurea but with inadequate glycemic control (A1C 7.5% to 11%) were enrolled in the trial. Those on metformin and sitagliptin (100 mg/day) directly entered the double-blind treatment period; those on another DPP-4 inhibitor and/or on a sulfonylurea entered a 4 to 8 week run-in period in which they were maintained on metformin and switched to sitagliptin (100 mg); other DPP-4 inhibitors and sulfonylureas were discontinued. At randomization patients were randomized either to continue sitagliptin or to discontinue sitagliptin and switch to a matching placebo. On the day of randomization, insulin glargine was initiated at a dose of 10 units subcutaneously in the evening. Patients were instructed to up-titrate their insulin dose in the evening based on fasting blood glucose measurements to achieve a target of 72 to100 mg/dL.

At 30 weeks, the mean reduction in A1C was greater in the sitagliptin group than in the placebo group (Table 14). At the end of the trial, 27.3% of patients in the sitagliptin group and 27.3% in the placebo group had a fasting plasma glucose (FPG) in the target range; there was no significant difference in insulin dose between arms.

Table 14: Change from Baseline in A1C and FPG at Week 30 in the Maintenance of Sitagliptin During Initiation and Titration of Insulin Glargine Trial
 | Sitagliptin 100 mg + Metformin + Insulin Glargine | Placebo + Metformin + Insulin Glargine
A1C (%) | N = 373 [N is the number of randomized and treated patients.] | N = 370
Baseline (mean) | 8.8 | 8.8
Week 30 (mean) | 6.9 | 7.3
Change from baseline (adjusted mean) [Analysis of Covariance including all post-baseline data regardless of rescue or treatment discontinuation. Model estimates calculated using multiple imputation to model washout of the treatment effect using placebo data for all subjects having missing Week 30 data.] | -1.9 | -1.4
Difference from placebo (adjusted mean) (95% CI) | -0.4 (-0.6, -0.3) [p<0.001 compared to placebo.]
Patients (%) with A1C <7% | 202 (54.2%) | 131 (35.4%)
FPG (mg/dL) | N = 373 | N = 370
Baseline (mean) | 199 | 201
Week 30 (mean) | 118 | 123
Change from baseline (adjusted mean) | -81 | -76

Sitagliptin Add-on Therapy vs. Glipizide Add-on Therapy in Patients with Type 2 Diabetes Mellitus Inadequately Controlled on Metformin Immediate-Release

The efficacy of sitagliptin was evaluated in a 52-week, double-blind, glipizide-controlled noninferiority trial in patients with type 2 diabetes mellitus. Patients not on treatment or on other antihyperglycemic agents entered a run-in treatment period of up to 12 weeks duration with metformin HCl immediate-release monotherapy (dose of ≥1,500 mg per day) which included washout of medications other than metformin immediate-release, if applicable. After the run-in period, those with inadequate glycemic control (A1C 6.5% to 10%) were randomized 1:1 to the addition of sitagliptin 100 mg once daily or glipizide for 52 weeks. Patients receiving glipizide were given an initial dosage of 5 mg/day and then electively titrated over the next 18 weeks to a maximum dosage of 20 mg/day as needed to optimize glycemic control. Thereafter, the glipizide dose was to be kept constant, except for down-titration to prevent hypoglycemia. The mean dose of glipizide after the titration period was 10 mg.

After 52 weeks, sitagliptin and glipizide had similar mean reductions from baseline in A1C in the intent-to-treat analysis (Table 15). These results were consistent with the per protocol analysis (Figure 2). A conclusion in favor of the non-inferiority of sitagliptin to glipizide may be limited to patients with baseline A1C comparable to those included in the trial (over 70% of patients had baseline A1C less than 8% and over 90% had A1C less than 9%).

Table 15: Glycemic Parameters in a 52-Week Trial Comparing Sitagliptin to Glipizide as Add-On Therapy in Patients Inadequately Controlled on Metformin Immediate-Release (Intent-to-Treat Population) *
 | Sitagliptin 100 mg + Metformin Immediate-Release | Glipizide + Metformin Immediate- Release
A1C (%) | N = 576 | N = 559
Baseline (mean) | 7.7 | 7.6
Change from baseline (adjusted mean†) | -0.5 | -0.6
FPG (mg/dL) | N = 583 | N = 568
Baseline (mean) | 166 | 164
Change from baseline (adjusted mean†) | -8 | -8
* The intent-to-treat analysis used the patients' last observation in the trial prior to discontinuation.
† Least squares means adjusted for prior antihyperglycemic therapy status and baseline A1C value.

Figure 2: Mean Change from Baseline for A1C (%) Over 52 Weeks in a Trial Comparing Sitagliptin to Glipizide as Add-On Therapy in Patients Inadequately Controlled on Metformin Immediate-Release (Per Protocol Population)*

* The per protocol population (mean baseline A1C of 7.5%) included patients without major protocol violations who had observations at baseline and at Week 52.

The incidence of hypoglycemia in the sitagliptin group (4.9%) was significantly (p<0.001) lower than that in the glipizide group (32%). Patients treated with sitagliptin exhibited a significant mean decrease from baseline in body weight compared to a significant weight gain in patients administered glipizide (-1.5 kg vs. + 1.1 kg).

16 HOW SUPPLIED/STORAGE AND HANDLING

Tablets supplied as follows:

Contents | Description | How Supplied | NDC
50 mg sitagliptin and 500 mg metformin HCl extended-release tablets | Light orange to beige colored, oval shaped, film-coated tablets debossed with "1804" on one side and plain on the other side. | Bottles of 60 tablets with child-resistant closure | NDC 70710-1804-6
50 mg sitagliptin and 1,000 mg metformin HCl extended-release tablets | Yellow to beige colored, oval shaped, film-coated tablets debossed with "1805" on one side and plain on the other side. | Bottles of 60 tablets with child-resistant closure | NDC 70710-1805-6
100 mg sitagliptin and 1,000 mg metformin HCl extended-release tablets | Reddish brown to brown colored, oval shaped, film-coated tablets debossed with "1806" on one side and plain on the other side. | Bottles of 30 tablets with child-resistant closure | NDC 70710-1806-3

Store at 20°C to 25°C (68°F to 77°F); excursions permitted to 15°C to 30°C (59°F to 86°F) [see USP Controlled Room Temperature]. Store in a dry place with cap tightly closed. Keep ZITUVIMET XR in the original container to protect it from moisture. Use ZITUVIMET XR within 1 month of opening the bottle.

17 PATIENT COUNSELING INFORMATION

Advise the patient to read the FDA-approved patient labeling (Medication Guide).

Lactic Acidosis

Explain the risks of lactic acidosis, its symptoms, and conditions that predispose to its development. Advise patients to discontinue ZITUVIMET XR immediately and to promptly notify their healthcare provider if unexplained hyperventilation, myalgias, malaise, unusual somnolence or other nonspecific symptoms occur. Counsel patients against excessive alcohol intake and inform patients about the importance of regular testing of renal function while receiving ZITUVIMET XR. Instruct patients to inform their doctor that they are taking ZITUVIMET XR prior to any surgical or radiological procedure, as temporary discontinuation may be required [see Warnings and Precautions (5.1)].

Pancreatitis

Inform patients that acute pancreatitis has been reported during postmarketing use of ZITUVIMET XR. Inform patients that persistent severe abdominal pain, sometimes radiating to the back, which may or may not be accompanied by vomiting, is the hallmark symptom of acute pancreatitis. Instruct patients to promptly discontinue ZITUVIMET XR and contact their physician if persistent severe abdominal pain occurs [see Warnings and Precautions (5.2)].

Heart Failure

Inform patients of the signs and symptoms of heart failure. Before initiating ZITUVIMET XR, ask patients about a history of heart failure or other risk factors for heart failure including moderate to severe renal impairment. Instruct patients to contact their health care provider as soon as possible if they experience symptoms of heart failure, including increasing shortness of breath, rapid increase in weight or swelling of the feet [see Warnings and Precautions (5.3)].

Vitamin B12 Deficiency

Inform patients about the importance of regular monitoring of hematological parameters while receiving ZITUVIMET XR [see Warnings and Precautions (5.5)].

Hypoglycemia

Inform patients that the incidence of hypoglycemia is increased when ZITUVIMET XR is added to an insulin secretagogue (e.g., sulfonylurea) or insulin therapy. Explain to patients receiving ZITUVIMET XR in combination with these medications the risks of hypoglycemia, its symptoms and treatment and conditions that predispose to its development [see Warnings and Precautions (5.6)].

Hypersensitivity Reactions

Inform patients that allergic reactions have been reported during postmarketing use of sitagliptin, one of the components of ZITUVIMET XR. If symptoms of allergic reactions (including rash, hives, and swelling of the face, lips, tongue, and throat that may cause difficulty in breathing or swallowing) occur, patients must stop taking ZITUVIMET XR and seek medical advice promptly.

Severe and Disabling Arthralgia

Inform patients that severe and disabling joint pain may occur with this class of drugs. The time to onset of symptoms can range from one day to years. Instruct patients to seek medical advice if severe joint pain occurs [see Warnings and Precautions (5.8)].

Bullous Pemphigoid

Inform patients that bullous pemphigoid may occur with this class of drugs. Instruct patients to seek medical advice if blisters or erosions occur [see Warnings and Precautions (5.9)].

Administration Instructions

Inform patients that the tablets must be swallowed whole and never split, crushed or chewed.

Incompletely Dissolved Tablets in Feces

Inform patients that incompletely dissolved ZITUVIMET XR tablets may be eliminated in the feces. Tell patients that, if they repeatedly see tablets in feces, they should report this finding to their health care provider. Assess adequacy of glycemic control if a patient reports repeatedly observing tablets in feces.

Females of Reproductive Age:

Inform females that treatment with ZITUVIMET XR may result in ovulation in some premenopausal anovulatory women which may lead to unintended pregnancy [see Use in Specific Populations (8.3)].

Medication Guide available at www.zydususa.com/medguides or call 1-877-993-8779.

The trademarks depicted herein are owned by their respective companies.

Manufactured by:

Zydus Lifesciences Ltd.

Pharmez, Matoda, Ahmedabad, India

Distributed by:

Zydus Pharmaceuticals (USA) Inc.

Route 31 North, Pennington, NJ 08534

Rev:.07/25

SPL MEDGUIDE

Medication Guide
ZITUVIMET® XR (zye too' vi met XR)
(sitagliptin and metformin hydrochloride extended-release)
tablets, for oral use

Read this Medication Guide carefully before you start taking ZITUVIMET XR and each time you get a refill. There may be new information. This information does not take the place of talking with your health care provider about your medical condition or your treatment. If you have any questions about ZITUVIMET XR, ask your health care provider or pharmacist.

What is the most important information I should know about ZITUVIMET XR?
ZITUVIMET XR can cause serious side effects, including:
Lactic Acidosis. Metformin, one of the medicines in ZITUVIMET XR, can cause a rare but serious condition called lactic acidosis (a buildup of an acid in the blood) that can cause death. Lactic acidosis is a medical emergency and must be treated in the hospital.
Stop taking ZITUVIMET XR and call your health care provider right away if you have any of the following symptoms, which could be signs of lactic acidosis:

- you feel cold in your hands or feet
- you feel dizzy or lightheaded
- you have a slow or irregular heartbeat
- you feel very weak or tired
- you have unusual (not normal) muscle pain
- you have trouble breathing
- you feel sleepy or drowsy
- you have stomach pains, nausea or vomiting

Most people who have had lactic acidosis with metformin have other things that, combined with the metformin, led to the lactic acidosis. Tell your health care provider if you have any of the following, because you have a higher chance for getting lactic acidosis with ZITUVIMET XR if you:

- have severe kidney problems or your kidneys are affected by certain x-ray tests that use injectable dye
- have liver problems
- drink alcohol very often, or drink a lot of alcohol in short-term "binge" drinking
- get dehydrated (lose a large amount of body fluids). This can happen if you are sick with a fever, vomiting, or diarrhea. Dehydration can also happen when you sweat a lot with activity or exercise and do not drink enough fluids.
- have surgery
- have a heart attack, severe infection, or stroke
- are 65 years of age or older

The best way to keep from having a problem with lactic acidosis from metformin is to tell your health care provider if you have any of the problems in the list above. Your health care provider may decide to stop your ZITUVIMET XR for a while if you have any of these things.
ZITUVIMET XR can have other serious side effects. See " What are the possible side effects of ZITUVIMET XR? "
Inflammation of the pancreas (pancreatitis) which may be severe and lead to death. Certain medical problems make you more likely to get pancreatitis.
Before you start taking ZITUVIMET XR, tell your health care provider if you have ever had:

- pancreatitis
- stones in your gallbladder (gallstones)
- high blood triglyceride levels
- a history of alcoholism
- kidney problems

Stop taking ZITUVIMET XR and call your health care provider right away if you have pain in your stomach area (abdomen) that is severe and will not go away. The pain may be felt going from your abdomen through to your back. The pain may happen with or without vomiting. These may be symptoms of pancreatitis.
Heart failure. Heart failure means that your heart does not pump blood well enough.
Before you start taking ZITUVIMET XR, tell your health care provider if you have ever had heart failure or have problems with your kidneys. Contact your health care provider right away if you have any of the following symptoms:

- increasing shortness of breath or trouble breathing, especially when you lie down
- swelling or fluid retention, especially in the feet, ankles or legs
- an unusually fast increase in weight
- unusual tiredness

These may be symptoms of heart failure.

What is ZITUVIMET XR?

- ZITUVIMET XR is a prescription medicine that contains 2 prescription diabetes medicines, sitagliptin and extended-release metformin hydrochloride. ZITUVIMET XR is used along with diet and exercise to lower blood sugar in adults with type 2 diabetes.
- ZITUVIMET XR is not for people with type 1 diabetes.
- If you have had pancreatitis (inflammation of the pancreas) in the past, it is not known if you have a higher chance of getting pancreatitis while you take ZITUVIMET XR.
- It is not known if ZITUVIMET XR is safe and effective in children

Who should not take ZITUVIMET XR?
Do not take ZITUVIMET XR if you:

- have severe kidney problems.
- have diabetic ketoacidosis.
- are allergic to any of the ingredients in ZITUVIMET XR. See the end of this Medication Guide for a complete list of ingredients in ZITUVIMET XR.

Symptoms of a serious allergic reaction to ZITUVIMET XR may include rash, raised red patches on your skin (hives) or swelling of the face, lips, tongue, and throat that may cause difficulty in breathing or swallowing.

What should I tell my health care provider before taking ZITUVIMET XR?
Before you take ZITUVIMET XR, tell your health care provider about all of your medical conditions, including if you:

- have or have had inflammation of your pancreas (pancreatitis).
- have kidney problems.
- have liver problems.
- have heart failure.
- drink alcohol very often or drink a lot of alcohol in short-term "binge" drinking.
- are going to get an injection of dye or contrast agents for an x-ray procedure. ZITUVIMET XR may need to be stopped for a short time. Talk to your health care provider about when you should stop ZITUVIMET XR and when you should start ZITUVIMET XR again. See "What is the most important information I should know about ZITUVIMET XR?".
- have low levels of vitamin B12 in your blood.
- are pregnant, think you may be pregnant, or plan to become pregnant. It is not known if ZITUVIMET XR will harm your unborn baby. If you are pregnant, talk with your health care provider about the best way to control your blood sugar while you are pregnant.
- are breastfeeding or plan to breastfeed. It is not known if ZITUVIMET XR will pass into your breast milk. Talk with your health care provider about the best way to feed your baby if you are taking ZITUVIMET XR.
- are a woman who has not gone through menopause (premenopausal) who does not have periods regularly or at all. ZITUVIMET XR can cause the release of an egg from an ovary in a woman (ovulation). This can increase your chance of getting pregnant. Tell your health care provider right away if you become pregnant while taking ZITUVIMET XR.

Tell your health care provider about all the medicines you take, including prescription and over-the-counter medicines, vitamins, and herbal supplements. ZITUVIMET XR may affect the way other medicines work and other medicines may affect how ZITUVIMET XR works.
Know the medicines you take. Keep a list of your medicines and show it to your health care provider and pharmacist when you get a new medicine.

How should I take ZITUVIMET XR?

- Take ZITUVIMET XR 1 time each day by mouth. Your health care provider will tell you exactly how many ZITUVIMET XR tablets to take and when you should take them.
- Take ZITUVIMET XR with meals to help to lower your chance of having an upset stomach.

Take ZITUVUMET XR tablets whole. Do not break or cut ZITUVIMET XR tablets before swallowing. If you cannot swallow ZITUVIMET XR tablets whole, tell your health care provider.

- Your health care provider may tell you to take ZITUVIMET XR along with certain other diabetes medicines. Low blood sugar (hypoglycemia) can happen more often when ZITUVIMET XR is taken with certain other diabetes medicines. See "What are the possible side effects of ZITUVIMET XR?"
- When your body is under some types of stress, such as fever, trauma (such as a car accident), infection or surgery, the amount of diabetes medicine that you need may change. Tell your health care provider right away. if you have any of these problems and follow your health care provider's instructions.
- Your health care provider will do blood tests to check how well your kidneys are working before and during your treatment with ZITUVIMET XR.
- If you miss a dose, take it with food as soon as you remember. If you do not remember until it is time for your next dose, skip the missed dose and go back to your regular schedule. Do not take 2 doses of ZITUVIMET XR at the same time.
- You may need to stop taking ZITUVIMET XR for a short time. Call your health care provider for instructions if you:
- are dehydrated (have lost too much body fluid). Dehydration can occur if you are sick with severe vomiting, diarrhea or fever, or if you drink a lot less fluid than normal.
- If you take too much ZITUVIMET XR, call your health care provider or Poison Help Line at 1-800-222-1222 or go to the nearest hospital emergency room right away.

What are the possible side effects of ZITUVIMET XR?
ZITUVIMET XR may cause serious side effects, including:

- See "What is the most important information I should know about ZITUVIMET XR?"
- Kidney problems, sometimes requiring dialysis.
- Low vitamin B12 (vitamin B12 deficiency). Using metformin for long periods of time may cause a decrease in the amount of vitamin B12 in your blood, especially if you have had low vitamin B12 blood levels before. Your health care provider may do blood tests to check your vitamin B12 levels.
- Low blood sugar (hypoglycemia). If you take ZITUVIMET XR with another medicine that can cause low blood sugar, such as a sulfonylurea or insulin, your risk of getting low blood sugar is higher. The dose of your sulfonylurea medicine or insulin may need to be lowered while you use ZITUVIMET XR. Signs and symptoms of low blood sugar may include:

- headache

- irritability

- dizziness

- sweating

- weakness

- drowsiness

- hunger

- confusion

- feeling jittery

- fast heart beat

- Serious allergic reactions. If you have any symptoms of a serious allergic reaction, stop taking ZITUVIMET XR and call your health care provider right away or get emergency medical help. See "Who should not take ZITUVIMET XR?". Your health care provider may give you a medicine for your allergic reaction and prescribe a different medicine for your diabetes.
- Joint pain. Some people who take medicines called DPP-4 inhibitors, one of the medicines in ZITUVIMET XR, may develop joint pain that can be severe. Call your health care provider if you have severe joint pain.
- Skin reaction. Some people who take medicines called DPP-4 inhibitors, one of the medicines in ZITUVIMET XR, may develop a skin reaction called bullous pemphigoid that can require treatment in a hospital. Tell your health care provider right away if you develop blisters or the breakdown of the outer layer of your skin (erosion). Your health care provider may tell you to stop taking ZITUVIMET XR.

The most common side effects of ZITUVIMET XR include:

• diarrhea
• upper respiratory infection
• headache
Taking ZITUVIMET XR with meals can help lessen the common stomach side effects of metformin that usually happen at the beginning of treatment. If you have unusual or sudden stomach problems, talk with your health care provider. Stomach problems that start later during treatment may be a sign of something more serious.
ZITUVIMET XR may have other side effects, including swelling of the hands or legs. Swelling of the hands and legs can happen if you take ZITUVIMET XR in combination with rosiglitazone (Avandia). Rosiglitazone is another type of diabetes medicine.
Tell your health care provider if you have any side effect that bothers you or does not go away.
These are not all the possible side effects of ZITUVIMET XR. For more information, ask your health care provider or pharmacist.
Call your doctor for medical advice about side effects. You may report side effects to FDA at 1-800-FDA-1088.

How should I store ZITUVIMET XR?

- Store ZITUVIMET XR in the original container at room temperature, between 68°F to 77°F (20°C to 25°C).
- Keep ZITUVIMET XR in the original container to protect it from moisture
- Use ZITUVIMET XR within 1 month of opening the bottle.

Keep ZITUVIMET XR and all medicines out of the reach of children.

General information about the safe and effective use of ZITUVIMET XR.
Medicines are sometimes prescribed for purposes other than those listed in a Medication Guide. Do not use ZITUVIMET XR for a condition for which it was not prescribed. Do not give ZITUVIMET XR to other people, even if they have the same symptoms you have. It may harm them.
This Medication Guide summarizes the most important information about ZITUVIMET XR. If you would like to know more information, talk with your health care provider. You can ask your health care provider or pharmacist for information about ZITUVIMET XR that is written for health professionals.

What are the ingredients in ZITUVIMET XR?
Active ingredients: sitagliptin and metformin hydrochloride
Inactive ingredients:

- All doses of ZITUVIMET XR Tablets contain: colloidal silicon dioxide, croscarmellose sodium, dibasic calcium phosphate anhydrous, ferric oxide yellow, hypromellose, magnesium stearate, malic acid, microcrystalline cellulose, povidone, pregelatinized starch (maize) and sodium stearyl fumarate. In addition, the film-coating for all doses contains the following inactive ingredients: polyethylene glycol, polyvinyl alcohol-partially hydrolyzed, iron oxide yellow, talc and titanium dioxide.
- Additionally, ZITUVIMET XR 50 mg/500 mg and 100 mg/1,000 mg tablets film-coating contain the inactive ingredient red iron oxide and 50 mg/1,000 mg and 100 mg/1,000 mg tablets film-coating contain the FD&C yellow#6 Aluminum Lake.

For more information, go to MedicalAffairs@zydususa.com or call 1-877-993-8779.
Medication Guide available at www.zydususa.com/medguides or call 1-877-993-8779.
The trademarks depicted herein are owned by their respective companies.

Manufactured by:
Zydus Lifesciences Ltd.
Pharmez, Matoda, Ahmedabad, India
Distributed by:
Zydus Pharmaceuticals (USA) Inc.
Route 31 North, Pennington, NJ 08534

Approved.: 07/2025

This Medication Guide has been approved by the U.S. Food and Drug Administration.

PACKAGE LABEL.PRINCIPAL DISPLAY PANEL

NDC 70710-1804-6

ZITUVIMET XR (sitagliptin and metformin hydrochloride extended-release) tablets

50 mg/500 mg

60 Tablets

Rx only

NDC 70710-1805-6

ZITUVIMET XR (sitagliptin and metformin hydrochloride extended-release) tablets

50 mg/1,000 mg

60 Tablets

Rx only

NDC 70710-1806-3

ZITUVIMET XR (sitagliptin and metformin hydrochloride extended-release) tablets

100 mg/1,000 mg

30 Tablets

Rx only